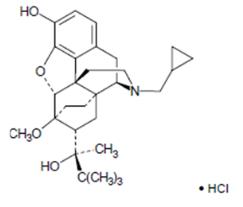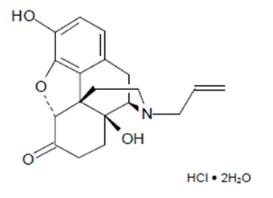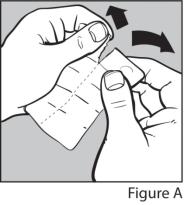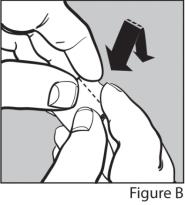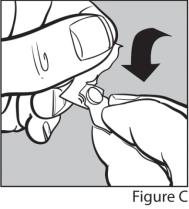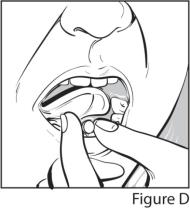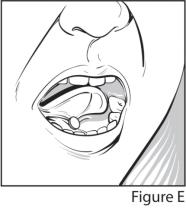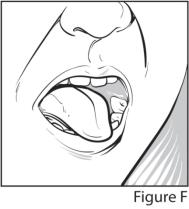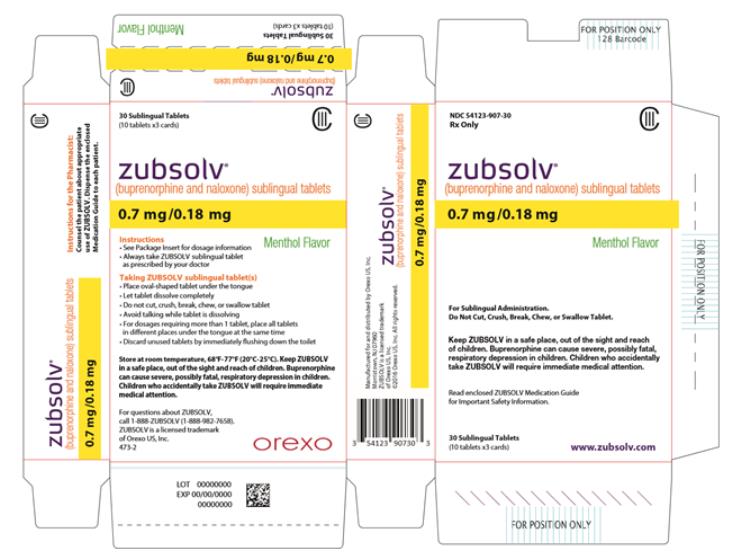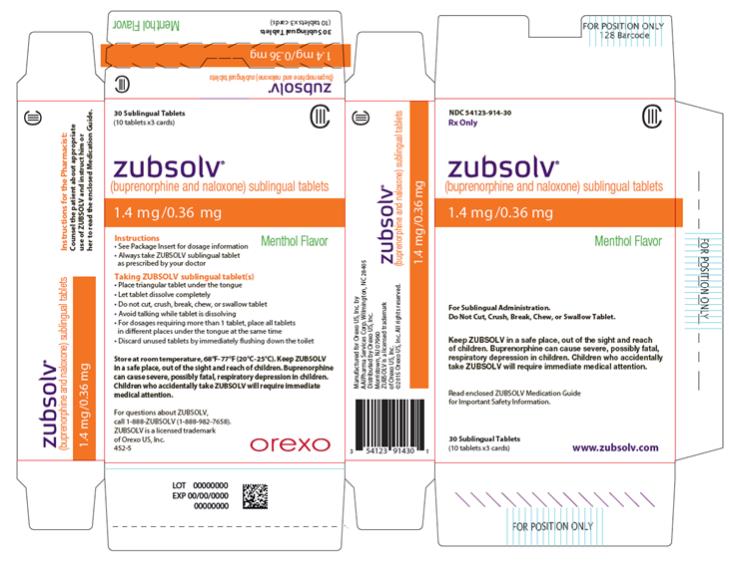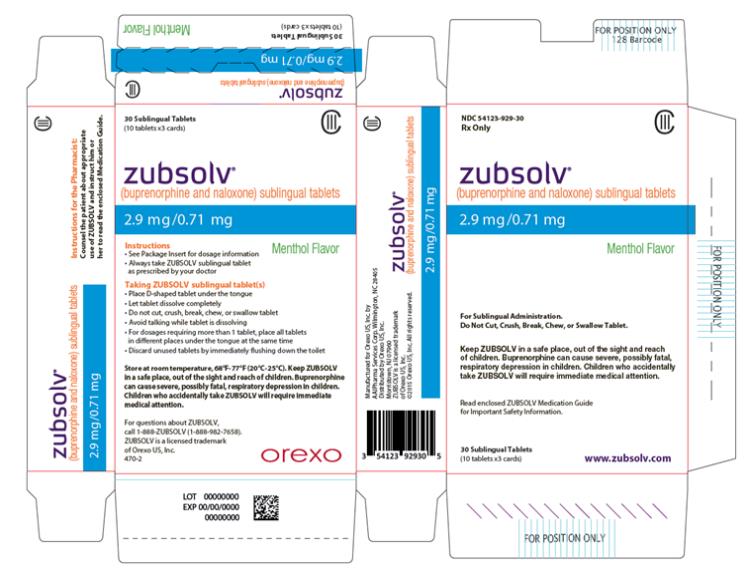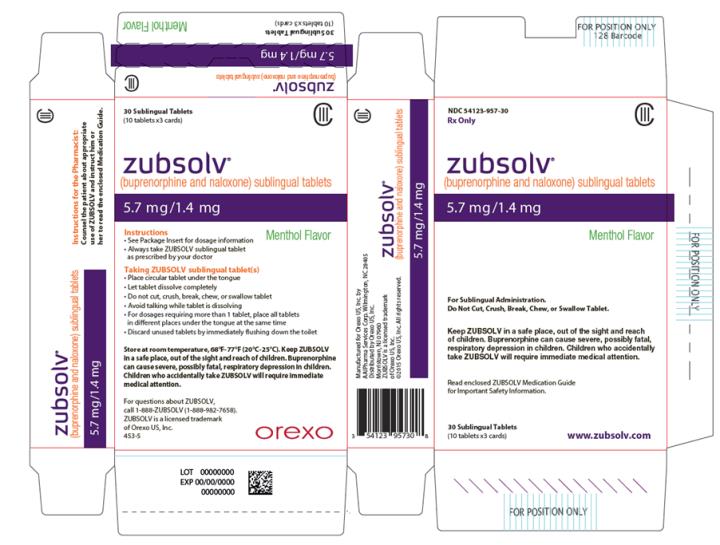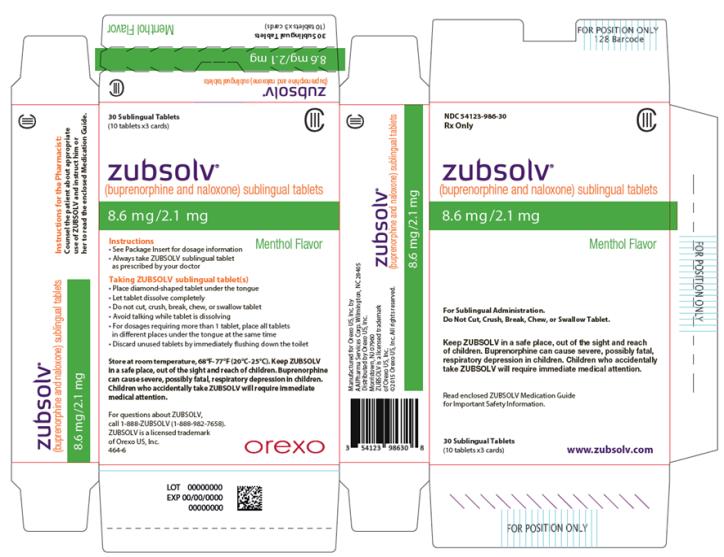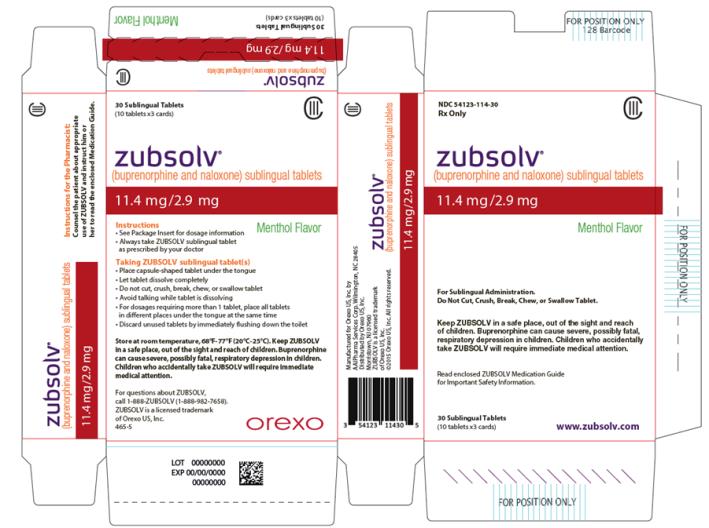 DRUG LABEL: Zubsolv
NDC: 54123-907 | Form: TABLET, ORALLY DISINTEGRATING
Manufacturer: Orexo US, Inc.
Category: prescription | Type: HUMAN PRESCRIPTION DRUG LABEL
Date: 20251227
DEA Schedule: CIII

ACTIVE INGREDIENTS: BUPRENORPHINE HYDROCHLORIDE 0.7 mg/1 1; NALOXONE HYDROCHLORIDE 0.18 mg/1 1
INACTIVE INGREDIENTS: MANNITOL; CITRIC ACID MONOHYDRATE; SODIUM CITRATE; MICROCRYSTALLINE CELLULOSE; CROSCARMELLOSE SODIUM; SUCRALOSE; SILICON DIOXIDE; SODIUM STEARYL FUMARATE; MENTHOL

HIGHLIGHTS OF PRESCRIBING INFORMATION

These highlights do not include all the information needed to use ZUBSOLV® safely and effectively. See full prescribing information for ZUBSOLV.
ZUBSOLV (buprenorphine and naloxone sublingual tablets), CIII
Initial U.S. Approval: 2002

RECENT MAJOR CHANGES

Dosage and Administration (2.2) 12/2025

Dosage and Administration (2.4) 05/2025

Warnings and Precautions (5.2, 5.3) 12/2025

1 INDICATIONS AND USAGE

ZUBSOLV contains buprenorphine, a partial opioid agonist, and naloxone, an opioid antagonist, and is indicated for treatment of opioid dependence. (1)

ZUBSOLV should be used as part of a complete treatment plan that includes counseling and psychosocial support. (1)

2 DOSAGE AND ADMINISTRATION

- Following induction, ZUBSOLV is administered sublingually as a single daily dose. (2.1)
- Strongly consider recommending or prescribing an opioid overdose reversal agent (e.g., naloxone, nalmefene) at the time ZUBSOLV is initiated or renewed because patients being treated for opioid use disorder have the potential for relapse, putting them at risk for opioid overdose. (2.2)
- To avoid precipitating withdrawal, induction with ZUBSOLV should be undertaken when objective and clear signs of withdrawal are evident and Zubsolv should be administered in divided doses when used as initial treatment. (2.3)
- For patients dependent on short-acting opioid products who are in opioid withdrawal; on Day 1, administer up to 5.7 mg/1.4 mg of Zubsolv (in divided doses). On Day 2, administer up to a total dose of 11.4 mg/2.9 mg of Zubsolv as a single dose. (2.3)
- For patients dependent on methadone or long-acting opioid products, induction onto sublingual buprenorphine monotherapy is recommended on Days 1 and 2 of treatment. (2.3)
- The maintenance dose of ZUBSOLV is generally in the range of 2.9 mg/0.71 mg to 17.2 mg/4.2 mg per day and should be based on clinical response. (2.4)
- Administer Zubsolv as directed in the Full Prescribing Information. (2.5)
- When discontinuing treatment, gradually taper to avoid signs and symptoms of withdrawal. (2.8)

3 DOSAGE FORMS AND STRENGTHS

Sublingual tablet:

- Buprenorphine 0.7 mg /naloxone 0.18 mg,
- Buprenorphine 1.4 mg /naloxone 0.36 mg,
- Buprenorphine 2.9 mg /naloxone 0.71 mg,
- Buprenorphine 5.7 mg /naloxone 1.4 mg,
- Buprenorphine 8.6 mg /naloxone 2.1 mg and
- Buprenorphine 11.4 mg /naloxone 2.9 mg. (3)

4 CONTRAINDICATIONS

Hypersensitivity to buprenorphine or naloxone. (4)

5 WARNINGS AND PRECAUTIONS

- Addiction, Abuse, and Misuse: Buprenorphine can be abused in a similar manner to other opioids. Monitor patients for conditions indicative of diversion or progression of opioid dependence and addictive behaviors. Multiple refills should not be prescribed early in treatment or without appropriate patient follow-up visits. (5.1)
- Respiratory Depression: Life-threatening respiratory depression and death have occurred in association with buprenorphine use. Warn patients of the potential danger of self-administration of benzodiazepines or other CNS depressants while under treatment with ZUBSOLV. (5.2, 5.3)
- Unintentional Pediatric Exposure: Store ZUBSOLV safely out of the sight and reach of children. Buprenorphine can cause severe and fatal respiratory depression in children. (5.4)
- Neonatal Opioid Withdrawal Syndrome: Neonatal opioid withdrawal syndrome (NOWS) is an expected and treatable outcome of prolonged use of opioids during pregnancy. (5.5)
- Adrenal Insufficiency: If diagnosed, treat with physiologic replacement of corticosteroids, and wean patient off of the opioid. (5.6)
- Risk of Opioid Withdrawal with Abrupt Discontinuation: If treatment is temporarily interrupted or discontinued, monitor patients for withdrawal and treat appropriately. (5.7)
- Risk of Hepatitis; Hepatic Events: Monitor liver function tests prior to initiation and during treatment and evaluate suspected hepatic events. (5.8)
- Precipitation of Opioid Withdrawal Signs and Symptoms: An opioid withdrawal syndrome is likely to occur with parenteral misuse of ZUBSOLV by individuals physically dependent on full opioid agonists or by sublingual administration before the agonist effects of other opioids have subsided. (5.10)
- Risk of Overdose in Opioid-Naïve Patients: ZUBSOLV is not appropriate as an analgesic. There have been reported deaths of opioid naïve individuals who received a 2 mg equivalent sublingual dose of buprenorphine. (5.11)

6 ADVERSE REACTIONS

Adverse events commonly observed with sublingual administration of ZUBSOLV are headache, nausea, vomiting, hyperhidrosis, constipation, signs and symptoms of withdrawal, insomnia, pain, and peripheral edema. (6)

To report SUSPECTED ADVERSE REACTIONS, contact Orexo at 1-888-982-7658, or FDA at 1-800-FDA-1088, or www.fda.gov/medwatch.

7 DRUG INTERACTIONS

- Benzodiazepines: Use caution in prescribing ZUBSOLV for patients receiving benzodiazepines or other CNS depressants and warn patients against concomitant self-administration/misuse. (7)
- CYP3A4 Inhibitors and Inducers: Monitor patients starting or ending CYP3A4 inhibitors or inducers for potential over or under dosing. (7)
- Antiretrovirals: Patients who are on chronic buprenorphine treatment should have their dose monitored if NNRTIs are added to their treatment regimen. Monitor patients taking buprenorphine and atazanavir with and without ritonavir, and reduce dose of buprenorphine if warranted. (7)
- Serotonergic Drugs: Concomitant use may result in serotonin syndrome. Discontinue ZUBSOLV if serotonin syndrome is suspected. (7)

8 USE IN SPECIFIC POPULATIONS

- Lactation: Buprenorphine passes into mother’s milk. (8.2)
- Geriatric Patients: Monitor for sedation and Respiratory Depression. (8.5)
- Moderate and Severe Hepatic Impairment: Buprenorphine/naloxone products are not recommended in patients with severe hepatic impairment and may not be appropriate for patients with moderate hepatic impairment. (8.6)

FULL PRESCRIBING INFORMATION

1 INDICATIONS AND USAGE

ZUBSOLV is indicated for treatment of opioid dependence. ZUBSOLV should be used as part of a complete treatment plan that includes counseling and psychosocial support.

2 DOSAGE AND ADMINISTRATION

2.1 Important Dosage and Administration Information

The difference in bioavailability of ZUBSOLV compared to Suboxone® sublingual tablet requires a different tablet strength to be given to the patient. One ZUBSOLV 5.7 mg/1.4 mg sublingual tablet provides equivalent buprenorphine exposure to one Suboxone 8 mg/2 mg sublingual tablet.

Medication should be prescribed in consideration of the frequency of visits. Provision of multiple refills is not advised early in treatment or without appropriate patient follow-up visits.

2.2 Patient Access to an Opioid Overdose Reversal Agent for the Emergency Treatment of Opioid Overdose

Inform patients and caregivers about opioid overdose reversal agents (e.g., naloxone, nalmefene) and discuss the importance of having access to an opioid overdose reversal agent. Because patients being treated for opioid use disorder have the potential for relapse, putting them at risk for opioid overdose, strongly consider recommending or prescribing an overdose reversal agent for the emergency treatment of opioid overdose, both when initiating and renewing treatment with ZUBSOLV. Also consider recommending or prescribing such an agent if the patient has household members (including children) or other close contacts at risk for accidental ingestion or opioid overdose [see Warnings and Precautions (5.2)].

Discuss the options for obtaining an opioid overdose reversal agent (e.g., prescription, over-the-counter, or as part of a community-based program) [see Warnings and Precautions (5.2)].

There are important differences among the opioid overdose reversal agents, such as route of administration, product strength, approved patient age range, and pharmacokinetics. Be familiar with these differences, as outlined in the approved labeling for those products, prior to recommending or prescribing such an agent.

Advise patients and caregivers that opioid overdose reversal agents, such as naloxone or nalmefene, may also be administered for a known or suspected overdose with ZUBSOLV itself. Higher than normal doses and repeated administration of an opioid overdose reversal agent may be necessary due to the long duration of action of ZUBSOLV and its affinity for the mu receptor [see Overdosage (10)].

2.3 Induction

Prior to induction, consideration should be given to the type of opioid dependence i.e., long- or short-acting opioid products, the time since last opioid use, and the degree or level of opioid dependence.

Patients dependent on heroin or other short-acting opioid products

Patients dependent on heroin or other short-acting opioid products may be induced with either ZUBSOLV or with sublingual buprenorphine monotherapy. At treatment initiation, the first dose of ZUBSOLV should be administered when objective signs of moderate opioid withdrawal appear, not less than six hours after the patient last used opioids, to avoid precipitating an opioid withdrawal syndrome.

It is recommended that an adequate treatment dose, titrated to clinical effectiveness, be achieved as rapidly as possible. In some studies, a too-gradual induction over several days led to a high rate of drop-out of buprenorphine patients during the induction period.

On Day 1, an induction dosage of up to 5.7 mg/1.4 mg ZUBSOLV is recommended. Clinicians should start with an initial dose of 1.4 mg/0.36 mg ZUBSOLV. The remainder of the Day 1 dose of up to 4.2 mg/1.08 mg should be divided into doses of 1 to 2 tablets of 1.4 mg/0.36 mg at 1.5 to 2 hour intervals. Some patients (e.g., those with recent exposure to buprenorphine) may tolerate up to 3 x 1.4 mg/0.36 mg ZUBSOLV as a single, second dose.

On Day 2, a single daily dose of up to 11.4 mg/2.9 mg ZUBSOLV is recommended.

Patients dependent on methadone or long-acting opioid products

Patients dependent on methadone or long-acting opioid products may be more susceptible to precipitated and prolonged withdrawal during induction than those on short-acting opioid products.

Buprenorphine/naloxone combination products have not been evaluated in adequate and well-controlled studies for induction in patients who are physically dependent on long-acting opioid products, and the naloxone in these combination products is absorbed in small amounts by the sublingual route and could cause worse precipitated and prolonged withdrawal. For this reason, buprenorphine monotherapy is recommended in patients taking long-acting opioids when used according to approved administration instructions. Following induction, the patient may then be transitioned to once-daily ZUBSOLV.

2.4 Maintenance

- The dosage of ZUBSOLV from Day 3 onwards should be progressively adjusted in increments/decrements of 2.9 mg/0.71 mg or lower of buprenorphine/naloxone to a level that holds the patient in treatment and suppresses opioid withdrawal signs and symptoms.
- After treatment induction to the recommended dose of 11.4 mg/2.9 mg buprenorphine/naloxone per day, dosing should be further adjusted based on the individual patient and clinical response. The maintenance dose of ZUBSOLV is generally in the range of 2.9 mg/0.71 mg buprenorphine/naloxone to 17.2 mg/4.2 mg buprenorphine/naloxone per day. Dosages higher than 17.2 mg/4.2 mg buprenorphine/naloxone daily have not been investigated in randomized clinical trials but may be appropriate for some patients.
- When determining the prescription quantity for unsupervised administration, consider the patient’s level of stability, the security of his or her home situation, and other factors likely to affect the ability to manage supplies of take-home medication.
- There is no maximum recommended duration of maintenance treatment. Patients may require treatment indefinitely and should continue for as long as patients are benefiting and the use of ZUBSOLV contributes to the intended treatment goals.

2.5 Method of Administration

ZUBSOLV must be administered whole. Do not cut, chew, or swallow ZUBSOLV. Advise patients not to eat or drink anything until the tablet is completely dissolved. ZUBSOLV should be placed under the tongue until dissolved. The dissolve time for ZUBSOLV varies between individuals, and the median dissolve time observed was 5 minutes. For dosages requiring more than one sublingual tablet, place all tablets in different places under the tongue at the same time. Patients should keep the tablets under the tongue until dissolved; swallowing the tablets reduces the bioavailability of the drug. To ensure consistency in bioavailability, patients should follow the same manner of dosing with continued use of the product.

If a sequential mode of administration is preferred, patients should follow the same manner of dosing to ensure consistency in bioavailability.

Proper administration technique should be demonstrated to the patient.

Advise patients to do the following after the product has completely dissolved in the oral mucosa: take a sip of water, swish gently around the teeth and gums, and swallow. Advise patients to wait for at least one hour after taking Zubsolv before brushing teeth [see Warnings and Precautions (5.13.), Postmarketing Experience (6.2), Information for Patients (17), and the Medication Guide].

2.6 Clinical Supervision

Treatment should be initiated with supervised administration, progressing to unsupervised administration as the patient’s clinical stability permits. ZUBSOLV is subject to diversion and abuse. When determining the prescription quantity for unsupervised administration, consider the patient’s level of stability, the security of his or her home situation, and other factors likely to affect the ability to manage supplies of take-home medication.

Ideally patients should be seen at reasonable intervals (e.g., at least weekly during the first month of treatment) based upon the individual circumstances of the patient. Medication should be prescribed in consideration of the frequency of visits. Provision of multiple refills is not advised early in treatment or without appropriate patient follow-up visits. Periodic assessment is necessary to determine compliance with the dosing regimen, effectiveness of the treatment plan, and overall patient progress.

Once a stable dosage has been achieved and patient assessment (e.g., urine drug screening) does not indicate illicit drug use, less frequent follow-up visits may be appropriate. A once-monthly visit schedule may be reasonable for patients on a stable dosage of medication who are making progress toward their treatment objectives. Continuation or modification of pharmacotherapy should be based on the healthcare provider’s evaluation of treatment outcomes and objectives such as:

1. Absence of medication toxicity
2. Absence of medical or behavioral adverse effects
3. Responsible handling of medications by the patient
4. Patient’s compliance with all elements of the treatment plan (including recovery-oriented activities, psychotherapy, and/or other psychosocial modalities)
5. Abstinence from illicit drug use (including problematic alcohol and/or benzodiazepine use)

If treatment goals are not being achieved, the healthcare provider should re-evaluate the appropriateness of continuing the current treatment.

2.7 Unstable Patients

Healthcare providers will need to decide when they cannot appropriately provide further management for particular patients. For example, some patients may be abusing or dependent on various drugs, or unresponsive to psychosocial intervention such that the healthcare provider does not feel that he/she has the expertise to manage the patient. In such cases, the healthcare provider may want to assess whether to refer the patient to a specialist or more intensive behavioral treatment environment. Decisions should be based on a treatment plan established and agreed upon with the patient at the beginning of treatment.

Patients who continue to misuse, abuse, or divert buprenorphine products or other opioids should be provided with, or referred to, more intensive and structured treatment.

2.8 Discontinuing Treatment

The decision to discontinue therapy with ZUBSOLV after a period of maintenance should be made as part of a comprehensive treatment plan. Advise patients of the potential to relapse to illicit drug use following discontinuation of opioid agonist/partial agonist medication-assisted treatment. Taper patients to avoid the occurrence of withdrawal signs and symptoms [see Warnings and Precautions (5.7)].

2.9 Switching between ZUBSOLV Sublingual Tablets and Other Buprenorphine/Naloxone Combination Products

For patients being switched between ZUBSOLV and other buprenorphine/naloxone products dosage adjustments may be necessary. Patients should be monitored for over-medication as well as withdrawal or other signs of under-dosing.

The differences in bioavailability of ZUBSOLV compared to Suboxone tablet require that different tablet strengths be given to the patient. One ZUBSOLV 5.7 mg/1.4 mg sublingual tablet provides equivalent buprenorphine exposure to one Suboxone 8 mg/2 mg sublingual tablet.

When switching between Suboxone dosage strengths and ZUBSOLV dosage strengths the corresponding dosage strengths are:

Suboxone sublingual tablets, including generic equivalents | Corresponding dosage strength of ZUBSOLV sublingual tablets
One 2 mg/0.5 mg sublingual buprenorphine/naloxone tablet | One 1.4 mg/0.36 mg ZUBSOLV sublingual tablet
4 mg/1 mg buprenorphine/naloxone taken as: • Two 2 mg/0.5 mg sublingual buprenorphine/naloxone tablets | One 2.9 mg/0.71 mg ZUBSOLV sublingual tablet
One 8 mg/2 mg sublingual buprenorphine/naloxone tablet | One 5.7 mg/1.4 mg ZUBSOLV sublingual tablet
12 mg/3 mg buprenorphine/naloxone, taken as: • One 8 mg/2 mg sublingual buprenorphine/naloxone tablet AND • Two 2 mg/0.5 mg sublingual buprenorphine/naloxone tablets | One 8.6 mg/2.1 mg ZUBSOLV sublingual tablet
16 mg/4 mg buprenorphine/naloxone, taken as: • Two 8 mg/2 mg sublingual buprenorphine/naloxone tablets | One 11.4 mg/2.9 mg ZUBSOLV sublingual tablet

3 DOSAGE FORMS AND STRENGTHS

ZUBSOLV sublingual tablet is supplied in six dosage strengths:

- Buprenorphine 0.7 mg /naloxone 0.18 mg, white, oval shape tablets imprinted with “.7”
- Buprenorphine 1.4 mg /naloxone 0.36 mg, white, triangular shape tablets imprinted with “1.4”
- Buprenorphine 2.9 mg /naloxone 0.71 mg, white, D shape tablets imprinted with “2.9”
- Buprenorphine 5.7 mg /naloxone 1.4 mg, white, round shape tablets imprinted with “5.7”
- Buprenorphine 8.6 mg /naloxone 2.1 mg, white, diamond shape tablets imprinted with “8.6”
- Buprenorphine 11.4 mg /naloxone 2.9 mg, white, capsule shape tablets imprinted with “11.4”

4 CONTRAINDICATIONS

ZUBSOLV is contraindicated in patients with a history of hypersensitivity to buprenorphine or naloxone as serious adverse reactions, including anaphylactic shock, have been reported [see Warnings and Precautions (5.9)].

5 WARNINGS AND PRECAUTIONS

5.1 Addiction, Abuse and Misuse

ZUBSOLV contains buprenorphine, a schedule III controlled substance that can be abused in a manner similar to other opioids, legal or illicit. Prescribe and dispense buprenorphine with appropriate precautions to minimize risk of misuse, abuse, or diversion, and ensure appropriate protection from theft, including in the home. Clinical monitoring appropriate to the patient’s level of stability is essential. Multiple refills should not be prescribed early in treatment or without appropriate patient follow-up visits [see Drug Abuse and Dependence (9.2)].

5.2 Risk of Life-Threatening Respiratory and Central Nervous System (CNS) Depression

Buprenorphine has been associated with life-threatening respiratory depression and death. Many, but not all, post-marketing reports regarding coma and death involved misuse by self-injection or were associated with the concomitant use of buprenorphine and benzodiazepines or other CNS depressants, including alcohol. Warn patients of the potential danger of self-administration of benzodiazepines or other CNS depressants while under treatment with ZUBSOLV [see Warnings and Precautions (5.3), Drug Interactions (7)].

Use ZUBSOLV with caution in patients with compromised respiratory function (e.g., chronic obstructive pulmonary disease, cor pulmonale, decreased respiratory reserve, hypoxia, hypercapnia, or pre-existing respiratory depression).

Educate patients and caregivers on how to recognize respiratory depression and emphasize the importance of calling 911 or getting emergency medical help right away in the event of a known or suspected overdose [see Patient Counseling Information (17)].

Opioids can cause sleep-related breathing disorders including central sleep apnea (CSA) and sleep-related hypoxemia. Opioid use increases the risk of CSA in a dose-dependent fashion. In patients who present with CSA, consider decreasing the opioid dosage using best practices for opioid taper [see Dosage and Administration (2.8)].

Patient Access to an Opioid Overdose Reversal Agent for the Emergency Treatment of Opioid Overdose

Inform patients and caregivers about opioid overdose reversal agents (e.g., naloxone, nalmefene) and discuss the importance of having access to an opioid overdose reversal agent. Because patients being treated for opioid use disorder have the potential for relapse, putting them at risk for opioid overdose, strongly consider recommending or prescribing an opioid overdose reversal agent for the emergency treatment of an opioid overdose, both when initiating and renewing treatment with ZUBSOLV. Also consider recommending or prescribing such an agent if the patient has household members (including children) or other close contacts at risk for accidental ingestion or opioid overdose [see Dosage and Administration (2.2)].

Discuss the options for obtaining an opioid overdose reversal agent (e.g., prescription, over-the-counter, or as part of a community-based program).

There are important differences among the opioid overdose reversal agents, such as route of administration, product strength, approved patient age range, and pharmacokinetics. Be familiar with these differences, as outlined in the approved labeling for those products, prior to recommending or prescribing such an agent.

Advise patients and caregivers that an opioid overdose reversal agent, such as naloxone or nalmefene may also be administered for a known or suspected overdose with ZUBSOLV itself. Higher than normal doses and repeated administration of an opioid reversal agent may be necessary due to the long duration of action of ZUBSOLV and its affinity for the mu receptor [see Overdosage (10)].

Educate patients and caregivers on how to recognize respiratory depression, and how to use an opioid overdose reversal agent for the emergency treatment of opioid overdose. Emphasize the importance of calling 911 or getting emergency medical help, even if an opioid overdose reversal agent is administered.

5.3 Managing Risks from Concomitant Use of Benzodiazepines or Other CNS Depressants

Concomitant use of buprenorphine and benzodiazepines and/or other CNS depressants (e.g., alcohol, non-benzodiazepine sedative/hypnotics, anxiolytics, tranquilizers, muscle relaxants, general anesthetics, antipsychotics, gabapentinoids [gabapentin or pregabalin], and other opioids) increases the risk of adverse reactions including overdose, respiratory depression, and death. Medication-assisted treatment of opioid use disorder, however, should not be categorically denied to patients taking these drugs. Prohibiting or creating barriers to treatment can pose an even greater risk of morbidity and mortality due to the opioid use disorder alone.

As a routine part of orientation to buprenorphine treatment, educate patients about the risks of concomitant use of benzodiazepines, sedatives, opioid analgesics, and alcohol.

Develop strategies to manage use of prescribed or illicit benzodiazepines or other CNS depressants at initiation of buprenorphine treatment, or if it emerges as a concern during treatment. Adjustments to induction procedures and additional monitoring may be required. There is no evidence to support dose limitations or arbitrary caps of buprenorphine as a strategy to address benzodiazepine use in buprenorphine-treated patients. However, if a patient is sedated at the time of buprenorphine dosing, delay or omit the buprenorphine dose if appropriate.

Cessation of benzodiazepines or other CNS depressants is preferred in most cases of concomitant use. In some cases, monitoring in a higher level of care for taper may be appropriate. In others, gradually tapering a patient off of a prescribed benzodiazepine or other CNS depressant or decreasing to the lowest effective dose may be appropriate.

For patients on buprenorphine treatment, benzodiazepines are not the treatment of choice for anxiety or insomnia. Before co-prescribing benzodiazepines, ensure that patients are appropriately diagnosed and consider alternative medications and non-pharmacologic treatments to address anxiety or insomnia. Ensure that other healthcare providers prescribing benzodiazepines or other CNS depressants are aware of the patient’s buprenorphine treatment and coordinate care to minimize the risks associated with concomitant use.

If concomitant use is warranted, strongly consider recommending or prescribing an opioid overdose reversal agent, as is recommended for all patients on buprenorphine treatment for opioid use disorder [see Dosage and Administration (2.2), Warnings and Precautions (5.2), Overdosage (10)].

In addition, take measures to confirm that patients are taking their medications as prescribed and are not diverting or supplementing with illicit drugs. Toxicology screening should test for prescribed and illicit benzodiazepines [see Drug Interactions (7)].

5.4 Unintentional Pediatric Exposure

Buprenorphine can cause fatal respiratory depression in children who are accidentally exposed to it. Store buprenorphine containing medications safely out of the sight and reach of children and destroy any unused medication appropriately [see Patient Counseling Information (17)].

5.5 Neonatal Opioid Withdrawal Syndrome

Neonatal opioid withdrawal syndrome (NOWS) is an expected and treatable outcome of prolonged use of opioids during pregnancy, whether that use is medically-authorized or illicit. Unlike opioid withdrawal syndrome in adults, NOWS may be life-threatening if not recognized and treated in the neonate. Healthcare professionals should observe newborns for signs of NOWS and manage accordingly [see Use in Specific Populations (8.1)].

Advise pregnant women receiving opioid addiction treatment with ZUBSOLV of the risk of neonatal opioid withdrawal syndrome and ensure that appropriate treatment will be available [see Use in Specific Populations (8.1)]. This risk must be balanced against the risk of untreated opioid addiction which often results in continued or relapsing illicit opioid use and is associated with poor pregnancy outcomes. Therefore, prescribers should discuss the importance and benefits of management of opioid addiction throughout pregnancy.

5.6 Adrenal Insufficiency

Cases of adrenal insufficiency have been reported with opioid use, more often following greater than one month of use. Presentation of adrenal insufficiency may include non-specific symptoms and signs including nausea, vomiting, anorexia, fatigue, weakness, dizziness, and low blood pressure. If adrenal insufficiency is suspected, confirm the diagnosis with diagnostic testing as soon as possible. If adrenal insufficiency is diagnosed, treat with physiologic replacement doses of corticosteroids. Wean the patient off of the opioid to allow adrenal function to recover and continue corticosteroid treatment until adrenal function recovers. Other opioids may be tried as some cases reported use of a different opioid without recurrence of adrenal insufficiency. The information available does not identify any particular opioids as being more likely to be associated with adrenal insufficiency.

5.7 Risk of Opioid Withdrawal with Abrupt Discontinuation

Buprenorphine is a partial agonist at the mu-opioid receptor and chronic administration produces physical dependence of the opioid type, characterized by withdrawal signs and symptoms upon abrupt discontinuation or rapid taper. The withdrawal syndrome is typically milder than seen with full agonists and may be delayed in onset. When discontinuing ZUBSOLV, gradually taper the dosage [see Dosage and Administration (2.8)].

5.8 Risk of Hepatitis, Hepatic Events

Cases of cytolytic hepatitis and hepatitis with jaundice have been observed in individuals receiving buprenorphine in clinical trials and through post-marketing adverse event reports. The spectrum of abnormalities ranges from transient asymptomatic elevations in hepatic transaminases to case reports of death, hepatic failure, hepatic necrosis, hepatorenal syndrome, and hepatic encephalopathy. In many cases, the presence of pre-existing liver enzyme abnormalities, infection with hepatitis B or hepatitis C virus, concomitant usage of other potentially hepatotoxic drugs, and ongoing injecting drug use may have played a causative or contributory role. In other cases, insufficient data were available to determine the etiology of the abnormality. Withdrawal of buprenorphine has resulted in amelioration of acute hepatitis in some cases; however, in other cases no dose reduction was necessary. The possibility exists that buprenorphine had a causative or contributory role in the development of the hepatic abnormality in some cases. Liver function tests, prior to initiation of treatment is recommended to establish a baseline. Periodic monitoring of liver function during treatment is also recommended. A biological and etiological evaluation is recommended when a hepatic event is suspected. Depending on the case, ZUBSOLV may need to be carefully discontinued to prevent withdrawal signs and symptoms and a return by the patient to illicit drug use, and strict monitoring of the patient should be initiated.

5.9 Hypersensitivity Reactions

Cases of hypersensitivity to buprenorphine and naloxone containing products have been reported both in clinical trials and in the post-marketing experience. Cases of bronchospasm, angioneurotic edema, and anaphylactic shock have been reported. The most common signs and symptoms include rashes, hives, and pruritus. A history of hypersensitivity to buprenorphine or naloxone is a contraindication to the use of ZUBSOLV.

5.10 Precipitation of Opioid Withdrawal Signs and Symptoms

Because it contains naloxone, ZUBSOLV is likely to produce withdrawal signs and symptoms if misused parenterally by individuals dependent on full opioid agonists such as heroin, morphine, or methadone. Because of the partial agonist properties of buprenorphine, ZUBSOLV may precipitate opioid withdrawal signs and symptoms in such persons if administered sublingually before the agonist effects of the opioid have subsided.

5.11 Risk of Overdose in Opioid Naïve Patients

There have been reported deaths of opioid naive individuals who received a 2 mg dose of buprenorphine as a sublingual tablet for analgesia. ZUBSOLV is not appropriate as an analgesic.

5.12 Use in Patients with Impaired Hepatic Function

Buprenorphine/naloxone products are not recommended in patients with severe hepatic impairment and may not be appropriate for patients with moderate hepatic impairment. The doses of buprenorphine and naloxone in this fixed-dose combination product cannot be individually titrated, and hepatic impairment results in a reduced clearance of naloxone to a much greater extent than buprenorphine. Therefore, patients with severe hepatic impairment will be exposed to substantially higher levels of naloxone than patients with normal hepatic function. This may result in an increased risk of precipitated withdrawal at the beginning of treatment (induction) and may interfere with buprenorphine’s efficacy throughout treatment. In patients with moderate hepatic impairment, the differential reduction of naloxone clearance compared to buprenorphine clearance is not as great as in subjects with severe hepatic impairment. However, buprenorphine/naloxone products are not recommended for initiation of treatment (induction) in patients with moderate hepatic impairment due to the increased risk of precipitated withdrawal. Buprenorphine/naloxone products may be used with caution for maintenance treatment in patients with moderate hepatic impairment who have initiated treatment on a buprenorphine product without naloxone. Patients should be carefully monitored and consideration given to the possibility of naloxone interfering with buprenorphine’s efficacy [see Use in Specific Populations (8.6)].

5.13 Dental Adverse Events

Cases of dental caries, some severe (i.e., tooth fracture, tooth loss), have been reported following the use of transmucosal buprenorphine-containing products. Reported events include cavities, tooth decay, dental abscesses/infection, rampant caries, tooth erosion, fillings falling out, and, in some cases, total tooth loss. Treatment for these events included tooth extraction, root canal, dental surgery, as well as other restorative procedures (i.e., fillings, crowns, implants, dentures). Multiple cases were reported in individuals without any prior history of dental problems.

Refer patients to dental care services and encourage them to have regular dental checkups while taking ZUBSOLV. Educate patients to seek dental care and strategies to maintain or improve oral health while being treated with transmucosal buprenorphine-containing products. Strategies include, but are not limited to, gently rinsing the teeth and gums with water and then swallowing after ZUBSOLV has been completely dissolved in the oral mucosa. Advise patients to wait for at least one hour after taking ZUBSOLV before brushing teeth [see Dosing and Administration (2.5), Information for Patients (17), Medication Guide].

5.14 QTc Prolongation

Thorough QT studies with buprenorphine products have demonstrated QT prolongation ≤15 msec. This QTc prolongation effect does not appear to be mediated by hERG channels. Based on these two findings, buprenorphine is unlikely to be pro-arrhythmic when used alone in patients without risk factors. The risk of combining buprenorphine with other QT prolonging agents is not known.

Consider these observations in clinical decisions when prescribing ZUBSOLV to patients with risk factors such as hypokalemia, bradycardia, recent conversion from atrial fibrillation, congestive heart failure, digitalis therapy, baseline QT prolongation, subclinical long-QT syndrome, or severe hypomagnesemia.

5.15 Impairment of Ability to Drive or Operate Machinery

ZUBSOLV may impair the mental or physical abilities required for the performance of potentially dangerous tasks such as driving a car or operating machinery, especially during treatment induction and dose adjustment. Caution patients about driving or operating hazardous machinery until they are reasonably certain that ZUBSOLV therapy does not adversely affect his or her ability to engage in such activities.

5.16 Orthostatic Hypotension

Like other opioids, ZUBSOLV may produce orthostatic hypotension in ambulatory patients.

5.17 Elevation of Cerebrospinal Fluid Pressure

Buprenorphine, like other opioids, may elevate cerebrospinal fluid pressure and should be used with caution in patients with head injury, intracranial lesions, and other circumstances when cerebrospinal pressure may be increased. Buprenorphine can produce miosis and changes in the level of consciousness that may interfere with patient evaluation.

5.18 Elevation of Intracholedochal Pressure

Buprenorphine has been shown to increase intracholedochal pressure, as do other opioids, and thus should be administered with caution to patients with dysfunction of the biliary tract.

5.19 Effects in Acute Abdominal Conditions

As with other opioids, buprenorphine may obscure the diagnosis or clinical course of patients with acute abdominal conditions.

6 ADVERSE REACTIONS

The following serious adverse reactions are described elsewhere in the labeling:

- Addiction, Abuse, and Misuse [see Warnings and Precautions (5.1)]
- Respiratory and CNS Depression [see Warnings and Precautions (5.2, 5.3)]
- Neonatal Opioid Withdrawal Syndrome [see Warnings and Precautions (5.5)]
- Adrenal Insufficiency [see Warnings and Precautions (5.6)]
- Opioid Withdrawal [see Warnings and Precautions (5.7, 5.10)]
- Hepatitis, Hepatic Events [see Warnings and Precautions (5.8)]
- Hypersensitivity Reactions [see Warnings and Precautions (5.9)]
- Orthostatic Hypotension [see Warnings and Precautions (5.16)]
- Elevation of Cerebrospinal Fluid Pressure [see Warnings and Precautions (5.17)]
- Elevation of Intracholedochal Pressure [see Warnings and Precautions (5.18)]

6.1 Clinical Trials Experience

Because clinical trials are conducted under widely varying conditions, adverse reaction rates observed in the clinical trials of a drug cannot be directly compared to rates in the clinical trials of another drug and may not reflect the rates observed in practice.

ZUBSOLV for use as initial treatment was evaluated in two clinical trials that had identical, blinded, two-day induction phases, comparing ZUBSOLV to generic buprenorphine. On the first day, subjects received an initial dose of ZUBSOLV 1.4 mg/0.36 mg or generic buprenorphine 2 mg, followed by ZUBSOLV 4.2 mg/1.08 mg or generic buprenorphine 6 mg 1.5 hours later. In total, safety data were available for 538 opioid-dependent subjects exposed to ZUBSOLV (buprenorphine/naloxone) sublingual tablets when used for initial treatment.

Table 1. Adverse Reactions in ≥ 5% of Patients During the Induction Phase by System Organ Class and Preferred Term (Safety Population)
System Organ Class Preferred Term | ZUBSOLV (N=538) | Generic BUP (N=530) | Overall (N=1068)
 | N (%)
Patients with any Adverse Reactions | 139 (26%) | 136 (26%) | 275 (26%)
Gastrointestinal Disorders | 64 (12%) | 60 (11%) | 124 (12%)
Nausea | 29 (5%) | 36 (7%) | 65 (6%)
Vomiting | 25 (5%) | 26 (5%) | 51 (5%)
Nervous System Disorders | 48 (9%) | 44 (8%) | 92 (9%)
Headache | 36 (7%) | 35 (7%) | 71 (7%)

BUP = buprenorphine

ZUBSOLV = buprenorphine/naloxone

The safety of buprenorphine/naloxone for longer-term use (up to 16 weeks of treatment) was evaluated in previous studies in 497 opioid-dependent subjects. The prospective evaluation of buprenorphine/naloxone was supported by clinical trials using buprenorphine tablets without naloxone and other trials using buprenorphine sublingual solutions. In total, safety data were available from 3214 opioid-dependent subjects exposed to buprenorphine at doses in the range used in treatment of opioid addiction. See Table 2.

Table 2. Adverse Events > 5% by Body System and Treatment Group in a 4-week Study
 | N (%) | N (%)
Body System / Adverse Event (COSTART Terminology) | Buprenorphine/ naloxone 16/4 mg/day N=107 | Placebo N=107
Body as a Whole
Asthenia | 7 (7%) | 7 (7%)
Chills | 8 (8%) | 8 (8%)
Headache | 39 (37%) | 24 (22%)
Infection | 6 (6%) | 7 (7%)
Pain | 24 (22%) | 20 (19%)
Pain Abdomen | 12 (11%) | 7 (7%)
Pain Back | 4 (4%) | 12 (11%)
Withdrawal Syndrome | 27 (25%) | 40 (37%)
Cardiovascular System
Vasodilation | 10 (9%) | 7 (7%)
Digestive System
Constipation | 13 (12%) | 3 (3%)
Diarrhea | 4 (4%) | 16 (15%)
Nausea | 16 (15%) | 12 (11%)
Vomiting | 8 (8%) | 5 (5%)
Nervous System
Insomnia | 15 (14%) | 17 (16%)
Respiratory System
Rhinitis | 5 (5%) | 14 (13%)
Skin and Appendages
Sweating | 15 (14%) | 11 (10%)

The adverse event profile of buprenorphine was also characterized in the dose-controlled study of buprenorphine solution, over a range of doses in four months of treatment. Table 3 shows adverse events reported by at least 5% of subjects in any dose group in the dose-controlled study.

Table 3. Adverse Events (≥ 5%) by Body System and Treatment Group in a 16-week Study
Body System /Adverse Event (COSTART Terminology) | Buprenorphine dose*
 | Very Low* (N=184) | Low* (N=180) | Moderate* (N=186) | High* (N=181) | Total* (N=731)
 | N (%) | N (%) | N (%) | N (%) | N (%)
Body as a Whole
Abscess | 9 (5%) | 2 (1%) | 3 (2%) | 2 (1%) | 16 (2%)
Asthenia | 26 (14%) | 28 (16%) | 26 (14%) | 24 (13%) | 104 (14%)
Chills | 11 (6%) | 12 (7%) | 9 (5%) | 10 (6%) | 42 (6%)
Fever | 7 (4%) | 2 (1%) | 2 (1%) | 10 (6%) | 21 (3%)
Flu Syndrome. | 4 (2%) | 13 (7%) | 19 (10%) | 8 (4%) | 44 (6%)
Headache | 51 (28%) | 62 (34%) | 54 (29%) | 53 (29%) | 220 (30%)
Infection | 32 (17%) | 39 (22%) | 38 (20%) | 40 (22%) | 149 (20%)
Injury Accidental | 5 (3%) | 10 (6%) | 5 (3%) | 5 (3%) | 25 (3%)
Pain | 47 (26%) | 37 (21%) | 49 (26%) | 44 (24%) | 177 (24%)
Pain Back | 18 (10%) | 29 (16%) | 28 (15%) | 27 (15%) | 102 (14%)
Withdrawal Syndrome | 45 (24%) | 40 (22%) | 41 (22%) | 36 (20%) | 162 (22%)
Digestive System
Constipation | 10 (5%) | 23 (13%) | 23 (12%) | 26 (14%) | 82 (11%)
Diarrhea | 19 (10%) | 8 (4%) | 9 (5%) | 4 (2%) | 40 (5%)
Dyspepsia | 6 (3%) | 10 (6%) | 4 (2%) | 4 (2%) | 24 (3%)
Nausea | 12 (7%) | 22 (12%) | 23 (12%) | 18 (10%) | 75 (10%)
Vomiting | 8 (4%) | 6 (3%) | 10 (5%) | 14 (8%) | 38 (5%)
Nervous System
Anxiety | 22 (12%) | 24 (13%) | 20 (11%) | 25 (14%) | 91 (12%)
Depression | 24 (13%) | 16 (9%) | 25 (13%) | 18 (10%) | 83 (11%)
Dizziness | 4 (2%) | 9 (5%) | 7 (4%) | 11 (6%) | 31 (4%)
Insomnia | 42 (23%) | 50 (28%) | 43 (23%) | 51 (28%) | 186 (25%)
Nervousness | 12 (7%) | 11 (6%) | 10 (5%) | 13 (7%) | 46 (6%)
Somnolence | 5 (3%) | 13 (7%) | 9 (5%) | 11 (6%) | 38 (5%)
Respiratory System
Cough Increase | 5 (3%) | 11 (6%) | 6 (3%) | 4 (2%) | 26 (4%)
Pharyngitis | 6 (3%) | 7 (4%) | 6 (3%) | 9 (5%) | 28 (4%)
Rhinitis | 27 (15%) | 16 (9%) | 15 (8%) | 21 (12%) | 79 (11%)
Skin and Appendages
Sweat | 23 (13%) | 21 (12%) | 20 (11%) | 23 (13%) | 87 (12%)
Special Senses
Runny Eyes | 13 (7%) | 9 (5%) | 6 (3%) | 6 (3%) | 34 (5%)

*Sublingual solution. Doses in this table cannot necessarily be delivered in tablet form, but for comparison purposes:

"Very low" dose (1 mg solution) would be less than a tablet dose of 2 mg
"Low" dose (4 mg solution) approximates a 6 mg tablet dose
"Moderate" dose (8 mg solution) approximates a 12 mg tablet dose
"High" dose (16 mg solution) approximates a 24 mg tablet dose

6.2 Post-marketing Experience

The following adverse reactions have been identified during post-approval use of buprenorphine and naloxone sublingual tablets. Because these reactions are reported voluntarily from a population of uncertain size, it is not always possible to reliably estimate a causal relationship to drug exposure.

The most frequently reported post-marketing adverse event not observed in clinical trials was peripheral edema.

Serotonin syndrome: Cases of serotonin syndrome, a potentially life-threatening condition, have been reported during concomitant use of opioids with serotonergic drugs.

Adrenal insufficiency: Cases of adrenal insufficiency have been reported with opioid use, more often following greater than one month of use.

Anaphylaxis: Anaphylaxis has been reported with ingredients contained in ZUBSOLV.

Androgen deficiency: Cases of androgen deficiency have occurred with chronic use of opioids [see Clinical Pharmacology (12.2)].

Local reactions: Dental decay (including caries, tooth fracture, and tooth loss),glossodynia, glossitis, oral mucosal erythema, oral hypoesthesia, and stomatitis.

Hypoglycemia: Cases of hypoglycemia have been reported in patients taking opioids. Most reports were in patients with at least one predisposing risk factor (e.g., diabetes).

Opioid-induced esophageal dysfunction (OIED): Cases of OIED have been reported in patients taking opioids, and may occur more frequently in patients taking higher doses of opioids, and/or in patients taking opioids longer term.

7 DRUG INTERACTIONS

Table 4 includes clinically significant drug interactions with ZUBSOLV.

Table 4. Clinically Significant Drug Interactions with ZUBSOLV
Benzodiazepines and other Central Nervous System (CNS) Depressants
Clinical Impact: | Due to additive pharmacologic effects, the concomitant use of benzodiazepines and other CNS depressants, including alcohol, increases the risk of respiratory depression, profound sedation, coma, and death.
Intervention: | Cessation of benzodiazepines or other CNS depressants is preferred in most cases of concomitant use. In some cases, monitoring in a higher level of care for taper may be appropriate. In others, gradually tapering a patient off of a prescribed benzodiazepine or other CNS depressant or decreasing to the lowest effective dose may be appropriate. Before co-prescribing benzodiazepines for anxiety or insomnia, ensure that patients are appropriately diagnosed and consider alternative medications and non-pharmacologic treatments [see Warnings and Precautions (5.2, 5.3)]. If concomitant use is warranted, strongly consider recommending or prescribing an opioid overdose reversal agent, as is recommended for all patients on buprenorphine treatment for opioid use disorder [see Warnings and Precautions (5.2)].
Examples: | Benzodiazepines and other sedatives/hypnotics, anxiolytics, tranquilizers, muscle relaxants, general anesthetics, antipsychotics, gabapentinoids (gabapentin or pregabalin), other opioids, alcohol.
Inhibitors of CYP3A4
Clinical Impact: | The concomitant use of buprenorphine and CYP3A4 inhibitors can increase the plasma concentration of buprenorphine, resulting in increased or prolonged opioid effects, particularly when an inhibitor is added after a stable dose of ZUBSOLV is achieved. After stopping a CYP3A4 inhibitor, as the effects of the inhibitor decline, the buprenorphine plasma concentration will decrease [see Clinical Pharmacology (12.3)], potentially resulting in decreased opioid efficacy or a withdrawal syndrome in patients who had developed physical dependence to buprenorphine.
Intervention: | If concomitant use is necessary, consider dosage reduction of ZUBSOLV until stable drug effects are achieved. Monitor patients for respiratory depression and sedation at frequent intervals. If a CYP3A4 inhibitor is discontinued, consider increasing the ZUBSOLV dosage until stable drug effects are achieved. Monitor for signs of opioid withdrawal.
Examples: | Macrolide antibiotics (e.g., erythromycin), azole-antifungal agents (e.g. ketoconazole), protease inhibitors (e.g., ritonavir).
CYP3A4 Inducers
Clinical Impact: | The concomitant use of buprenorphine and CYP3A4 inducers can decrease the plasma concentration of buprenorphine [see Clinical Pharmacology (12.3)], potentially resulting in decreased efficacy or onset of a withdrawal syndrome in patients who have developed physical dependence to buprenorphine. After stopping a CYP3A4 inducer, as the effects of the inducer decline, the buprenorphine plasma concentration will increase [see Clinical Pharmacology (12.3)], which could increase or prolong both therapeutic effects and adverse reactions and may cause serious respiratory depression.
Intervention: | If concomitant use is necessary, consider increasing the ZUBSOLV dosage until stable drug effects are achieved. Monitor for signs of opioid withdrawal. If a CYP3A4 inducer is discontinued, consider ZUBSOLV dosage reduction and monitor for signs of respiratory depression.
Examples: | Rifampin, carbamazepine, phenytoin.
Antiretrovirals: Non-Nucleoside Reverse Transcriptase inhibitors (NNRTIs)
Clinical Impact: | Non-nucleoside reverse transcriptase inhibitors (NNRTIs) are metabolized principally by CYP3A4. Efavirenz, nevirapine, and etravirine are known CYP3A inducers, whereas delavirdine is a CYP3A inhibitor. Significant pharmacokinetic interactions between NNRTIs (e.g., efavirenz and delavirdine) and buprenorphine have been shown in clinical studies, but these pharmacokinetic interactions did not result in any significant pharmacodynamic effects.
Intervention: | Patients who are on chronic ZUBSOLV treatment should have their dose monitored if NNRTIs are added to their treatment regimen.
Examples: | Efavirenz, nevirapine, etravirine, delavirdine.
Antiretrovirals: Protease Inhibitors (PIs)
Clinical Impact: | Studies have shown some antiretroviral protease inhibitors (PIs) with CYP3A4 inhibitory activity (nelfinavir, lopinavir/ritonavir, ritonavir) have little effect on buprenorphine pharmacokinetic and no significant pharmacodynamic effects. Other PIs with CYP3A4 inhibitory activity (atazanavir and atazanavir/ritonavir) resulted in elevated levels of buprenorphine and norbuprenorphine, and patients in one study reported increased sedation. Symptoms of opioid excess have been found in post-marketing reports of patients receiving buprenorphine and atazanavir with and without ritonavir concomitantly.
Intervention: | Monitor patients taking ZUBSOLV and atazanavir with and without ritonavir, and reduce dose of ZUBSOLV if warranted.
Examples: | Atazanavir, ritonavir.
Antiretrovirals: Nucleoside Reverse Transcriptase Inhibitors (NRTIs)
Clinical Impact: | Nucleoside reverse transcriptase inhibitors (NRTIs) do not appear to induce or inhibit the P450 enzyme pathway, thus no interactions with buprenorphine are expected.
Intervention: | None.
Serotonergic Drugs
Clinical Impact: | The concomitant use of opioids with other drugs that affect the serotonergic neurotransmitter system has resulted in serotonin syndrome.
Intervention: | If concomitant use is warranted, carefully observe the patient, particularly during treatment initiation and dose adjustment. Discontinue ZUBSOLV if serotonin syndrome is suspected.
Examples: | Selective serotonin reuptake inhibitors (SSRIs), serotonin and norepinephrine reuptake inhibitors (SNRIs), tricyclic antidepressants (TCAs), triptans, 5-HT3 receptor antagonists, drugs that effect the serotonin neurotransmitter system (e.g., mirtazapine, trazodone, tramadol), certain muscle relaxants (i.e., cyclobenzaprine, metaxalone), monoamine oxidase (MAO) inhibitors (those intended to treat psychiatric disorders and also others, such as linezolid and intravenous methylene blue).
Monoamine Oxidase Inhibitors (MAOIs)
Clinical Impact: | MAOI interactions with opioids may manifest as serotonin syndrome or opioid toxicity (e.g., respiratory depression, coma) [see Warnings and Precautions (5.2)]
Intervention: | The use of ZUBSOLV is not recommended for patients taking MAOIs or within 14 days of stopping such treatment.
Examples: | Phenelzine, tranylcypromine, linezolid.
Muscle Relaxants
Clinical Impact: | Buprenorphine may enhance the neuromuscular blocking action of skeletal muscle relaxants and produce an increased degree of respiratory depression.
Intervention: | Monitor patients receiving muscle relaxants and ZUBSOLV for signs of respiratory depression that may be greater than otherwise expected and decrease the dosage of ZUBSOLV and/or the muscle relaxant as necessary. Due to the risk of respiratory depression with concomitant use of skeletal muscle relaxants and opioids, strongly consider recommending or prescribing an opioid overdose reversal agent, as is recommended for all patients on buprenorphine treatment for opioid use disorder. [see Dosage and Administration (2.2), Warnings and Precautions (5.2, 5.3)].
Examples: | cyclobenzaprine, metaxalone
Diuretics
Clinical Impact: | Opioids can reduce the efficacy of diuretics by inducing the release of antidiuretic hormone.
Intervention: | Monitor patients for signs of diminished diuresis and/or effects on blood pressure and increase the dosage of the diuretic as needed.
Anticholinergic Drugs
Clinical Impact: | The concomitant use of anticholinergic drugs may increase the risk of urinary retention and/or severe constipation, which may lead to paralytic ileus.
Intervention: | Monitor patients for signs of urinary retention or reduced gastric motility when ZUBSOLV is used concomitantly with anticholinergic drugs.

8 USE IN SPECIFIC POPULATIONS

8.1 Pregnancy

Risk Summary

The data on use of buprenorphine, one of the active ingredients in ZUBSOLV, in pregnancy, are limited; however, these data do not indicate an increased risk of major malformations specifically due to buprenorphine exposure. There are limited data from randomized clinical trials in women maintained on buprenorphine that were not designed appropriately to assess the risk of major malformations [see Data]. Observational studies have reported on congenital malformations among buprenorphine-exposed pregnancies, but were also not designed appropriately to assess the risk of congenital malformations specifically due to buprenorphine exposure [see Data]. The extremely limited data on sublingual naloxone exposure in pregnancy are not sufficient to evaluate a drug-associated risk.

Reproductive and developmental studies in rats and rabbits identified adverse events at clinically relevant and higher doses. Embryofetal death was observed in both rats and rabbits administered buprenorphine during the period of organogenesis at doses approximately 6 and 0.3 times, respectively, the human sublingual dose of 16 mg/day of buprenorphine. Pre- and post-natal development studies in rats demonstrated increased neonatal deaths at 0.3 times and above and dystocia at approximately 3 times the human sublingual dose of 16 mg/day of buprenorphine. No clear teratogenic effects were seen when buprenorphine was administered during organogenesis with a range of doses equivalent to or greater than the human sublingual dose of 16 mg/day of buprenorphine. However, increases in skeletal abnormalities were noted in rats and rabbits administered buprenorphine daily during organogenesis at doses approximately 0.6 and approximately equal to the human sublingual dose of 16 mg/day of buprenorphine, respectively. In a few studies, some events such as acephalus and omphalocele were also observed but these findings were not clearly treatment-related [see Data]. Based on animal data, advise pregnant women of the potential risk to a fetus.

The estimated background risk of major birth defects and miscarriage for the indicated population are unknown. All pregnancies have a background risk of birth defect, loss, or other adverse outcomes. In the U.S. general population, the estimated background risk of major birth defects and miscarriage in clinically recognized pregnancies is 2-4% and 15-20%, respectively.

Clinical Considerations

Disease-Associated Maternal and Embryo-fetal Risk

Untreated opioid addiction in pregnancy is associated with adverse obstetrical outcomes such as low birth weight, preterm birth, and fetal death. In addition, untreated opioid addiction often results in continued or relapsing illicit opioid use.

Dose Adjustment during Pregnancy and the Postpartum Period

Dosage adjustments of buprenorphine, such as using higher doses, may be required during pregnancy, even if the patient was maintained on a stable dose prior to pregnancy. Dosing should be based on individual response, and withdrawal signs and symptoms should be monitored closely and the dose adjusted as necessary.

Fetal/neonatal Adverse Reactions

Neonatal opioid withdrawal syndrome may occur in newborn infants of mothers who are receiving treatment with ZUBSOLV.

Neonatal opioid withdrawal syndrome presents as irritability, hyperactivity and abnormal sleep pattern, high pitched cry, tremor, vomiting, diarrhea, and/or failure to gain weight. Signs of neonatal withdrawal usually occur in the first days after birth. The duration and severity of neonatal opioid withdrawal syndrome may vary. Observe newborns for signs of neonatal opioid withdrawal syndrome and manage accordingly [see Warnings and Precautions (5.5)].

Labor or Delivery

Opioid-dependent women on buprenorphine maintenance therapy may require additional analgesia during labor.

Data

Human Data

Studies have been conducted to evaluate neonatal outcomes in women exposed to buprenorphine during pregnancy. Limited data from trials, observational studies, case series, and case reports on buprenorphine use in pregnancy do not indicate an increased risk of major malformations specifically due to buprenorphine. Several factors may complicate the interpretation of investigations of the children of women who take buprenorphine during pregnancy, including maternal use of illicit drugs, late presentation for prenatal care, infection, poor compliance, poor nutrition, and psychosocial circumstances. Interpretation of data is complicated further by the lack of information on untreated opioid-dependent pregnant women, who would be the most appropriate group for comparison. Rather, women on another form of opioid medication-assisted treatment, or women in the general population are generally used as the comparison group. However, women in these comparison groups may be different from women prescribed buprenorphine-containing products with respect to maternal factors that may lead to poor pregnancy outcomes.

In a multicenter, double-blind, randomized, controlled trial [Maternal Opioid Treatment: Human Experimental Research (MOTHER)] designed primarily to assess neonatal opioid withdrawal effects, opioid-dependent pregnant women were randomized to buprenorphine (n=86) or methadone (n=89) treatment, with enrollment at an average gestational age of 18.7 weeks in both groups. A total of 28 of the 86 women in the buprenorphine group (33%) and 16 of the 89 women in the methadone group (18%) discontinued treatment before the end of pregnancy.

Among women who remained in treatment until delivery, there was no difference between buprenorphine-treated and methadone-treated groups in the number of neonates requiring NOWS treatment or in the peak severity of NOWS. Buprenorphine-exposed neonates required less morphine (mean total dose, 1.1 mg vs. 10.4 mg), had shorter hospital stays (10.0 days vs. 17.5 days), and shorter duration of treatment for NOWS (4.1 days vs. 9.9 days) compared to the methadone-exposed group. There were no differences between groups in other primary outcomes (neonatal head circumference,) or secondary outcomes (weight and length at birth, preterm birth, gestational age at delivery, and 1-minute and 5-minute Apgar scores), or in the rates of maternal or neonatal adverse events. The outcomes among mothers who discontinued treatment before delivery and may have relapsed to illicit opioid use are not known. Because of the imbalance in discontinuation rates between the buprenorphine and methadone groups, the study findings are difficult to interpret.

Animal Data

ZUBSOLV has been shown to have differences in bioavailability compared to other buprenorphine/naloxone-containing sublingual products. The exposure margins listed below are based on body surface area comparisons (mg/m^2) to the human sublingual dose of 16 mg buprenorphine via Suboxone, which is equivalent to a human sublingual dose of 11.4 mg buprenorphine via ZUBSOLV.

Effects on embryo-fetal development were studied in Sprague-Dawley rats and Russian white rabbits following oral (1:1) and intramuscular (IM) (3:2) administration of mixtures of buprenorphine and naloxone during the period of organogenesis. Following oral administration to rats, no teratogenic effects were observed at buprenorphine doses up to 250 mg/kg/day (estimated exposure approximately 150 times the human sublingual dose of 16 mg) in the presence of maternal toxicity (mortality). Following oral administration to rabbits, no teratogenic effects were observed at buprenorphine doses up to 40 mg/kg/day (estimated exposure approximately 50 times the human sublingual dose of 16 mg) in the absence of clear maternal toxicity. No definitive drug-related teratogenic effects were observed in rats and rabbits at IM doses up to 30 mg/kg/day (estimated exposure approximately 20 times and 35 times, respectively, the human sublingual dose of 16 mg). Maternal toxicity resulting in mortality was noted in these studies in both rats and rabbits. Acephalus was observed in one rabbit fetus from the low-dose group and omphalocele was observed in two rabbit fetuses from the same litter in the mid-dose group; no findings were observed in fetuses from the high-dose group. Maternal toxicity was seen in the high-dose group but not at the lower doses where the findings were observed. Following oral administration of buprenorphine to rats, dose-related post-implantation losses, evidenced by increases in the numbers of early resorptions with consequent reductions in the numbers of fetuses, were observed at doses of 10 mg/kg/day or greater (estimated exposure approximately 6 times the human sublingual dose of 16 mg). In the rabbit, increased post-implantation losses occurred at an oral dose of 40 mg/kg/day. Following IM administration in the rat and the rabbit, post-implantation losses, as evidenced by decreases in live fetuses and increases in resorptions, occurred at 30 mg/kg/day.

Buprenorphine was not teratogenic in rats or rabbits after IM or subcutaneous (SC) doses up to 5 mg/kg/day (estimated exposure was approximately 3 and 6 times, respectively, the human sublingual dose of 16 mg), after IV doses up to 0.8 mg/kg/day (estimated exposure was approximately 0.5 times and equal to, respectively, the human sublingual dose of 16 mg), or after oral doses up to 160 mg/kg/day in rats (estimated exposure was approximately 95 times the human sublingual dose of 16 mg) and 25 mg/kg/day in rabbits (estimated exposure was approximately 30 times the human sublingual dose of 16 mg). Significant increases in skeletal abnormalities (e.g., extra thoracic vertebra or thoraco-lumbar ribs) were noted in rats after SC administration of 1 mg/kg/day and up (estimated exposure was approximately 0.6 times the human sublingual dose of 16 mg), but were not observed at oral doses up to 160 mg/kg/day. Increases in skeletal abnormalities in rabbits after IM administration of 5 mg/kg/day (estimated exposure was approximately 6 times the human daily sublingual dose of 16 mg) in the absence of maternal toxicity or oral administration of 1 mg/kg/day or greater (estimated exposure was approximately equal to the human sublingual dose of 16 mg) were not statistically significant.

In rabbits, buprenorphine produced statistically significant pre-implantation losses at oral doses of 1 mg/kg/day or greater and post-implantation losses that were statistically significant at IV doses of 0.2 mg/kg/day or greater (estimated exposure approximately 0.3 times the human sublingual dose of 16 mg). No maternal toxicity was noted at doses causing post-implantation loss in this study.

Dystocia was noted in pregnant rats treated intramuscularly with buprenorphine from Gestation Day 14 through Lactation Day 21 at 5 mg/kg/day (approximately 3 times the human sublingual dose of 16 mg). Fertility, pre-, and post-natal development studies with buprenorphine in rats indicated increases in neonatal mortality after oral doses of 0.8 mg/kg/day and up (approximately 0.5 times the human sublingual dose of 16 mg), after IM doses of 0.5 mg/kg/day and up (approximately 0.3 times the human sublingual dose of 16 mg), and after SC doses of 0.1 mg/kg/day and up (approximately 0.06 times the human sublingual dose of 16 mg). An apparent lack of milk production during these studies likely contributed to the decreased pup viability and lactation indices. Delays in the occurrence of righting reflex and startle response were noted in rat pups at an oral dose of 80 mg/kg/day (approximately 50 times the human sublingual dose of 16 mg).

8.2 Lactation

Risk Summary

Based on two studies in 13 lactating women, maintained on buprenorphine treatment, buprenorphine and its metabolite norbuprenorphine were present in low levels in human milk and available data have not shown adverse reactions in breastfed infants. There are no data on the combination product buprenorphine/naloxone in breastfeeding, however oral absorption of naloxone is limited. The developmental and health benefits of breastfeeding should be considered along with the mother’s clinical need for ZUBSOLV and any potential adverse effects on the breastfed child from the drug or from the underlying maternal condition.

Clinical Considerations

Advise the breastfeeding women taking buprenorphine products to monitor the infant for increased drowsiness and breathing difficulties.

Data

Data were consistent from two studies (N=13) of breastfeeding infants whose mothers were maintained on sublingual doses of buprenorphine ranging from 2.4 to 24 mg/day, showing that the infants were exposed to less than 1% of the maternal daily dose.

In a study of six lactating women who were taking a median sublingual buprenorphine dose of 0.29 mg/kg/day 5 to 8 days after delivery, breast milk provided a median infant dose of 0.42 mcg/kg/day of buprenorphine and 0.33 mcg/kg/day of norbuprenorphine, equal to 0.2% and 0.12%, respectively, of the maternal weight-adjusted dose (relative dose/kg (%) of norbuprenorphine was calculated from the assumption that buprenorphine and norbuprenorphine are equipotent).

Data from a study of seven lactating women who were taking a median sublingual buprenorphine dose of 7 mg/day an average of 1.12 months after delivery indicated that the mean milk concentrations (Cavg) of buprenorphine and norbuprenorphine were 3.65 mcg/L and 1.94 mcg/L respectively. Based on the study data, and assuming milk consumption of 150 mL/kg/day, an exclusively breastfed infant would receive an estimated mean absolute infant dose (AID) of 0.55 mcg/kg/day of buprenorphine and 0.29 mcg/kg/day of norbuprenorphine, or a mean relative infant dose (RID) of 0.38% and 0.18%, respectively, of the maternal weight-adjusted dose.

8.3 Females and Males of Reproductive Potential

Infertility

Chronic use of opioids may cause reduced fertility in females and males of reproductive potential. It is not known whether these effects on fertility are reversible [see Adverse Reactions (6.2), Nonclinical Toxicology (13.1)].

8.4 Pediatric Use

The safety and effectiveness of ZUBSOLV have not been established in pediatric patients. This product is not appropriate for the treatment of neonatal opioid withdrawal syndrome in neonates, because it contains naloxone, an opioid antagonist.

8.5 Geriatric Use

Clinical studies of buprenorphine/naloxone sublingual tablets did not include sufficient numbers of subjects aged 65 and over to determine whether they responded differently than younger subjects. Other reported clinical experience have not identified differences in responses between the elderly and younger patients. Due to possible decreased hepatic, renal, or cardiac function and of concomitant disease or other drug therapy in geriatric patients, the decision to prescribe ZUBSOLV should be made cautiously in individuals 65 years of age or older and these patients should be monitored for signs and symptoms of toxicity or overdose.

8.6 Hepatic Impairment

The effect of hepatic impairment on the pharmacokinetics of buprenorphine and naloxone has been evaluated in a pharmacokinetic study. Both drugs are extensively metabolized in the liver. While no clinically significant changes have been observed in subjects with mild hepatic impairment; the plasma levels have been shown to be higher and half-life values have been shown to be longer for both buprenorphine and naloxone in subjects with moderate and severe hepatic impairment. The magnitude of the effects on naloxone is greater than that on buprenorphine in both moderately and severely impaired subjects. The difference in magnitude of the effects on naloxone and buprenorphine are greater in subjects with severe hepatic impairment than in subjects with moderate hepatic impairment, and therefore the clinical impact of these effects is likely to be greater in patients with severe hepatic impairment than in patients with moderate hepatic impairment. Buprenorphine/naloxone products should be avoided in patients with severe hepatic impairment and may not be appropriate for patients with moderate hepatic impairment [see Warnings and Precautions (5.12), Clinical Pharmacology (12.3)].

8.7 Renal Impairment

No differences in buprenorphine pharmacokinetics were observed between 9 dialysis-dependent and 6 normal patients following IV administration of 0.3 mg buprenorphine. The effects of renal failure on naloxone pharmacokinetics are unknown [see Clinical Pharmacology (12.3)].

9 DRUG ABUSE AND DEPENDENCE

9.1 Controlled Substance

ZUBSOLV contains buprenorphine, a Schedule III substance under the Controlled Substances Act.

9.2 Abuse

Buprenorphine, like morphine and other opioids, has the potential to be abused and is subject to criminal diversion. This should be considered when prescribing or dispensing buprenorphine in situations when the clinician is concerned about an increased risk of misuse, abuse, or diversion. Healthcare professionals should contact their state professional licensing board or state controlled substances authority for information on how to prevent and detect abuse or diversion of this product.

Patients who continue to misuse, abuse, or divert buprenorphine products or other opioids should be provided with, or referred to, more intensive and structured treatment.

Abuse of buprenorphine poses a risk of overdose and death. This risk is increased with the abuse of buprenorphine and alcohol and other substances, especially benzodiazepines.

The healthcare provider may be able to more easily detect misuse or diversion by maintaining records of medication prescribed including date, dose, quantity, frequency of refills, and renewal requests of medication prescribed.

Proper assessment of the patient, proper prescribing practices, periodic re-evaluation of therapy, and proper handling and storage of the medication are appropriate measures that help to limit abuse of opioid drugs.

9.3 Dependence

Buprenorphine is a partial agonist at the mu-opioid receptor and chronic administration produces physical dependence of the opioid type, characterized by moderate withdrawal signs and symptoms upon abrupt discontinuation or rapid taper. The withdrawal syndrome is typically milder than seen with full agonists and may be delayed in onset [see Warnings and Precautions (5.7)].

Neonatal opioid withdrawal syndrome (NOWS) is an expected and treatable outcome of prolonged use of opioids during pregnancy [see Warnings and Precautions (5.5)].

10 OVERDOSAGE

Clinical Presentation

The manifestations of acute buprenorphine overdose include pinpoint pupils, sedation, hypotension, hypoglycemia, respiratory depression, and death.

Toxic leukoencephalopathy has been reported after opioid overdose and can present hours, days, or weeks after apparent recovery from the initial intoxication.

Treatment of Overdose

In the event of overdose, the respiratory and cardiac status of the patient should be monitored carefully. When respiratory or cardiac functions are depressed, primary attention should be given to the re-establishment of adequate respiratory exchange through provision of a patent airway and institution of assisted or controlled ventilation. Oxygen, IV fluids, vasopressors, and other supportive measures should be employed as indicated.

In the case of overdose, the primary management should be the re-establishment of adequate ventilation with mechanical assistance of respiration, if required. An opioid overdose reversal agent may be of value for the management of buprenorphine overdose. Higher than normal doses and repeated administration may be necessary. The long duration of action of ZUBSOLV should be taken into consideration when determining the length of treatment and medical surveillance needed to reverse the effects of an overdose. Insufficient duration of monitoring may put patients at risk.

11 DESCRIPTION

ZUBSOLV (buprenorphine and naloxone) sublingual tablets are white menthol-flavored tablets in an oval shape for the dosage strength 0.7 mg/0.18 mg, a triangular shape for the dosage strength 1.4 mg /0.36 mg, a D shape for the dosage strength 2.9 mg/0.71 mg, a round shape for the dosage strength 5.7 mg/1.4 mg, a diamond shape for the dosage strength 8.6 mg/2.1 mg and a capsule shape for the dosage strength 11.4 mg/2.9 mg. They are debossed with the respective dosage strength of buprenorphine. They contain buprenorphine HCl, an opioid partial agonist and naloxone HCl dihydrate, an opioid antagonist, at a ratio of 4:1 (ratio of free bases). ZUBSOLV is intended for sublingual administration and is available in six dosage strengths, 0.7 mg buprenorphine with 0.18 mg naloxone, 1.4 mg buprenorphine with 0.36 mg naloxone, 2.9 mg buprenorphine with 0.71 mg naloxone, 5.7 mg buprenorphine with 1.4 mg naloxone, 8.6 mg buprenorphine with 2.1 mg naloxone and 11.4 mg buprenorphine with 2.9 mg naloxone. Each sublingual tablet also contains mannitol, citric acid, sodium citrate, microcrystalline cellulose, croscarmellose sodium, sucralose, menthol, silicon dioxide and sodium stearyl fumarate and menthol flavor.

Chemically, buprenorphine HCl is (2S)-2-[17-(cyclopropylmethyl)-4,5α-epoxy-3-hydroxy-6-methoxy-6α,14-ethano-14α-morphinan-7α-yl]-3,3-dimethylbutan-2-ol hydrochloride. It has the following chemical structure:

Buprenorphine HCl has the molecular formula C29 H41 NO4 • HCl and the molecular weight is 504.10. It is a white or off-white crystalline powder, sparingly soluble in water, freely soluble in methanol, soluble in alcohol, and practically insoluble in cyclohexane.

Chemically, naloxone HCl dihydrate is 17-Allyl-4,5α-epoxy-3,14-dihydroxymorphinan-6-one hydrochloride dihydrate. It has the following chemical structure:

Naloxone HCl dihydrate has the molecular formula C19H21NO4 • HCl • 2H20 and the molecular weight is 399.87. It is a white to slightly off-white powder and is freely soluble in water, soluble in alcohol, and practically insoluble in toluene and ether.

12 CLINICAL PHARMACOLOGY

12.1 Mechanism of Action

ZUBSOLV contains buprenorphine and naloxone. Buprenorphine is a partial agonist at the mu-opioid receptor and an antagonist at the kappa-opioid receptor. Naloxone is a potent antagonist at mu-opioid receptors and produces opioid withdrawal signs and symptoms, if administered parenterally, in individuals physically dependent on full opioid agonists.

12.2 Pharmacodynamics

ZUBSOLV has been shown to have different bioavailability compared to Suboxone tablet. One ZUBSOLV 5.7 mg/1.4 mg tablet provides equivalent buprenorphine exposure and 12% lower naloxone exposure to one Suboxone 8 mg/2 mg tablet. The pharmacodynamic information of other currently marketed buprenorphine/naloxone-containing sublingual products is not directly comparable on a mg basis to ZUBSOLV [see Dosage and Administration (2.9].

Subjective Effects

Comparisons of buprenorphine to full opioid agonists such as methadone and hydromorphone suggest that sublingual buprenorphine produces typical opioid agonist effects which are limited by a ceiling effect.

In opioid-experienced subjects who were not physically dependent, acute sublingual doses of Suboxone tablets produced opioid agonist effects which reached a maximum between doses of 8 mg/2 mg and 16 mg/4 mg buprenorphine/naloxone.

Opioid agonist ceiling-effects were also observed in a double-blind, parallel group, dose-ranging comparison of single doses of buprenorphine sublingual solution (1 mg, 2 mg, 4 mg, 8 mg, 16 mg, or 32 mg), placebo and a full agonist control at various doses. The treatments were given in ascending dose order at intervals of at least one week to 16 opioid-experienced subjects who were not physically dependent. Both active drugs produced typical opioid agonist effects. For all measures for which the drugs produced an effect, buprenorphine produced a dose-related response. However, in each case, there was a dose that produced no further effect. In contrast, the highest dose of the full agonist control always produced the greatest effects. Agonist objective rating scores remained elevated for the higher doses of buprenorphine (8 mg-32 mg) longer than for the lower doses and did not return to baseline until 48 hours after drug administration. The onset of effects appeared more rapidly with buprenorphine than with the full agonist control, with most doses nearing peak effect after 100 minutes for buprenorphine compared to 150 minutes for the full agonist control.

Physiologic Effects

Buprenorphine in IV (2 mg, 4 mg, 8 mg, 12 mg and 16 mg) and sublingual (12 mg) doses has been administered to opioid-experienced subjects who were not physically dependent to examine cardiovascular, respiratory, and subjective effects at doses comparable to those used for treatment of opioid dependence. Compared to placebo, there were no statistically significant differences among any of the treatment conditions for blood pressure, heart rate, respiratory rate, O2 saturation, or skin temperature across time. Systolic BP was higher in the 8 mg group than placebo (3-hour AUC values). Minimum and maximum effects were similar across all treatments. Subjects remained responsive to low voice and responded to computer prompts. Some subjects showed irritability, but no other changes were observed.

The respiratory effects of sublingual buprenorphine were compared with the effects of methadone in a double-blind, parallel group, dose ranging comparison of single doses of buprenorphine sublingual solution (1 mg, 2 mg, 4 mg, 8 mg, 16 mg, or 32 mg) and oral methadone (15 mg, 30 mg, 45 mg, or 60 mg) in non-dependent, opioid-experienced volunteers. In this study, hypoventilation not requiring medical intervention was reported more frequently after buprenorphine doses of 4 mg and higher than after methadone. Both drugs decreased O2 saturation to the same degree.

Effect of Naloxone

Physiologic and subjective effects following acute sublingual administration of buprenorphine tablets and Suboxone tablets were similar at equivalent dose levels of buprenorphine. Naloxone had no clinically significant effect when administered by the sublingual route, although blood levels of the drug were measurable. Buprenorphine/naloxone, when administered sublingually to an opioid-dependent cohort, was recognized as an opioid agonist, whereas when administered intramuscularly, combinations of buprenorphine with naloxone produced opioid antagonist actions similar to naloxone. This finding suggests that the naloxone in buprenorphine/naloxone tablets may deter injection of buprenorphine/naloxone tablets by persons with active substantial heroin or other full mu-opioid dependence. However, clinicians should be aware that some opioid-dependent persons, particularly those with a low level of full mu-opioid physical dependence or those whose opioid physical dependence is predominantly to buprenorphine, abuse buprenorphine/naloxone combinations by the intravenous or intranasal route. In methadone-maintained patients and heroin-dependent subjects, IV administration of buprenorphine/naloxone combinations precipitated opioid withdrawal signs and symptoms and was perceived as unpleasant and dysphoric. In morphine-stabilized subjects, intravenously administered combinations of buprenorphine with naloxone produced opioid antagonist and withdrawal signs and symptoms that were ratio-dependent; the most intense withdrawal signs and symptoms were produced by 2:1 and 4:1 ratios, less intense by an 8:1 ratio.

Effects on the Endocrine System

Opioids inhibit the secretion of adrenocorticotropic hormone (ACTH), cortisol, and luteinizing hormone (LH) in humans [see Adverse Reactions (6.2)]. They also stimulate prolactin, growth hormone (GH) secretion, and pancreatic secretion of insulin and glucagon.

Chronic use of opioids may influence the hypothalamic-pituitary-gonadal axis, leading to androgen deficiency that may manifest as low libido, impotence, erectile dysfunction, amenorrhea, or infertility. The causal role of opioids in the clinical syndrome of hypogonadism is unknown because the various medical, physical, lifestyle, and psychological stressors that may influence gonadal hormone levels have not been adequately controlled for in studies conducted to date. Patients presenting with symptoms of androgen deficiency should undergo laboratory evaluation [see Adverse Reactions (6.2)].

Cardiac Electrophysiology

Thorough QT studies with buprenorphine products have demonstrated QT prolongation ≤15 msec.

12.3 Pharmacokinetics

Absorption

Plasma levels of buprenorphine and naloxone increased with the sublingual dose of ZUBSOLV. There was wide inter-patient variability in the sublingual absorption of buprenorphine and naloxone, but within subjects the variability was low. Both Cmax and AUC of buprenorphine increased with the increase in dose (in the range of 1.4 mg to 11.4 mg), although the increase was not directly dose-proportional. Naloxone did not affect the pharmacokinetics of buprenorphine.

ZUBSOLV has been shown to have different bioavailability compared to Suboxone tablet. One ZUBSOLV 5.7 mg/1.4 mg tablet provides equivalent buprenorphine exposure and 12% lower naloxone exposure to one Suboxone 8 mg/2 mg tablet.

Distribution

Buprenorphine is approximately 96% protein bound, primarily to alpha and beta globulin.

Naloxone is approximately 45% protein bound, primarily to albumin.

Elimination Metabolism

Buprenorphine undergoes both N-dealkylation to norbuprenorphine and glucuronidation. The N-dealkylation pathway is mediated primarily by the CYP3A4. Norbuprenorphine, the major metabolite, can further undergo glucuronidation. Norbuprenorphine has been found to bind opioid receptors in-vitro; however, it has not been studied clinically for opioid-like activity. Naloxone undergoes direct glucuronidation to naloxone-3-glucuronide as well as N-dealkylation, and reduction of the 6-oxo group.

Excretion

A mass balance study of buprenorphine showed complete recovery of radiolabel in urine (30%) and feces (69%) collected up to 11 days after dosing. Almost all of the dose was accounted for in terms of buprenorphine, norbuprenorphine, and two unidentified buprenorphine metabolites. In urine, most of buprenorphine and norbuprenorphine was conjugated (buprenorphine, 1% free and 9.4% conjugated; norbuprenorphine, 2.7% free and 11% conjugated). In feces, almost all of the buprenorphine and norbuprenorphine were free (buprenorphine, 33% free and 5% conjugated; norbuprenorphine, 21% free and 2% conjugated).

When ZUBSOLV tablets are administered sublingually, buprenorphine has a mean elimination half-life from plasma ranging from 24 to 42 hours and naloxone has a mean elimination half-life from plasma ranging from 2 to 12 hours.

Drug Interaction Studies

CYP3A4 Inhibitors and Inducers

Buprenorphine has been found to be a CYP2D6 and CYP3A4 inhibitor and its major metabolite, norbuprenorphine, has been found to be a moderate CYP2D6 inhibitor in in-vitro studies employing human liver microsomes. However, the relatively low plasma concentrations of buprenorphine and norbuprenorphine resulting from therapeutic doses are not expected to raise significant drug-drug interaction concerns [see Drug Interactions (7)].

Specific Populations

Hepatic Impairment

In a pharmacokinetic study, the disposition of buprenorphine and naloxone were determined after administering a Suboxone 2.0 mg/0.5 mg (buprenorphine/naloxone) sublingual tablet in subjects with varied degrees of hepatic impairment as indicated by Child-Pugh criteria. The disposition of buprenorphine and naloxone in patients with hepatic impairment were compared to disposition in subjects with normal hepatic function.

In subjects with mild hepatic impairment, the changes in mean Cmax, AUC0-last, and half-life values of both buprenorphine and naloxone were not clinically significant. No dosing adjustment is needed in patients with mild hepatic impairment.

For subjects with moderate and severe hepatic impairment, mean Cmax, AUC0-last, and half-life values of both buprenorphine and naloxone were increased; the effects on naloxone are greater than that on buprenorphine (Table 5).

Table 5. Changes in Pharmacokinetic Parameters in Subjects with Moderate and Severe Hepatic Impairment

Hepatic Impairment | PK Parameters | Increase in buprenorphine compared to healthy subjects | Increase in naloxone compared to healthy subjects
Moderate | Cmax | 8% | 170%
 | AUC0-last | 64% | 218%
 | Half-life | 35% | 165%
Severe | Cmax | 72% | 1030%
 | AUC0-last | 181% | 1302%
 | Half-life | 57% | 122%

The difference in magnitude of the effects on naloxone and buprenorphine are greater in subjects with severe hepatic impairment than subjects with moderate hepatic impairment [see Warnings and Precautions (5.12) and Use in Specific Populations (8.6)].

HCV infection

In subjects with HCV infection but no sign of hepatic impairment, the changes in the mean Cmax, AUC0-last, and half-life values of buprenorphine and naloxone were not clinically significant in comparison to healthy subjects without HCV infection.

13 NONCLINICAL TOXICOLOGY

13.1 Carcinogenesis, Mutagenesis, Impairment of Fertility

ZUBSOLV has been shown to have differences in bioavailability compared to other buprenorphine/naloxone-containing sublingual products. The exposure margins listed below are based on body surface area comparisons (mg/m^2) to the recommended human sublingual dose of 16 mg buprenorphine via Suboxone, which is equivalent to a human sublingual dose of 11.4 mg buprenorphine via ZUBSOLV.

Carcinogenicity

A carcinogenicity study of buprenorphine/naloxone (4:1 ratio of the free bases) was performed in Alderley Park rats. Buprenorphine/naloxone was administered in the diet at doses of approximately 7 mg/kg/day, 31 mg/kg/day, and 123 mg/kg/day for 104 weeks (estimated exposure was approximately 4, 18, and 44 times the recommended human sublingual dose based on buprenorphine AUC comparisons). A statistically significant increase in Leydig cell adenomas was observed in all dose groups. No other drug-related tumors were noted.

Carcinogenicity studies of buprenorphine were conducted in Sprague-Dawley rats and CD-1 mice. Buprenorphine was administered in the diet to rats at doses of 0.6 mg/kg/day, 5.5 mg/kg/day, and 56 mg/kg/day (estimated exposure was approximately 0.4, 3, and 35 times the recommended human sublingual dose) for 27 months. As in the buprenorphine/naloxone carcinogenicity study in rat, statistically significant dose-related increases in Leydig cell tumors occurred. In an 86-week study in CD-1 mice, buprenorphine was not carcinogenic at dietary doses up to 100 mg/kg/day (estimated exposure was approximately 30 times the recommended human sublingual dose).

Mutagenicity

The 4:1 combination of buprenorphine and naloxone was not mutagenic in a bacterial mutation assay (Ames test) using four strains of S. typhimurium and two strains of E. coli. The combination was not clastogenic in an in vitro cytogenetic assay in human lymphocytes or in an IV micronucleus test in the rat.

Buprenorphine was studied in a series of tests utilizing gene, chromosome, and DNA interactions in both prokaryotic and eukaryotic systems. Results were negative in yeast (S. cerevisiae) for recombinant, gene convertant, or forward mutations; negative in Bacillus subtilis “rec” assay, negative for clastogenicity in CHO cells, Chinese hamster bone marrow and spermatogonia cells, and negative in the mouse lymphoma L5178Y assay.

Results were equivocal in the Ames test: negative in studies in two laboratories, but positive for frame shift mutation at a high dose (5 mg/plate) in a third study. Results were positive in the Green-Tweets (E. coli) survival test, positive in a DNA synthesis inhibition (DSI) test with testicular tissue from mice, for both in vivo and in vitro incorporation of [^3H]thymidine, and positive in unscheduled DNA synthesis (UDS) test using testicular cells from mice.

Impairment of Fertility

Dietary administration of buprenorphine in the rat at dose levels of 500 ppm or greater (equivalent to approximately 47 mg/kg/day or greater; estimated exposure approximately 28 times the recommended human sublingual dose) produced a reduction in fertility demonstrated by reduced female conception rates. A dietary dose of 100 ppm (equivalent to approximately 10 mg/kg/day; estimated exposure approximately 6 times the recommended human sublingual dose) had no adverse effect on fertility.

14 CLINICAL STUDIES

The induction of buprenorphine therapy with ZUBSOLV was evaluated in two blinded randomized, non-inferiority studies. The identical blinded induction phase component of the studies was designed to assess the tolerability of ZUBSOLV versus generic buprenorphine tablets when used as initial treatment, as measured by retention in treatment. The studies included opioid dependent (DSM-IV criteria) male and female patients 18 to 65 years of age. Induction doses for generic buprenorphine tablets were 8 mg for day 1 and 8 mg or 16 mg for day 2. The induction doses for ZUBSOLV were 5.7 mg/1.4 mg for day 1 and 5.7 mg/1.4 mg or 11.4 mg/2.8 mg for day 2. In the first study, 758 patients were randomized. In the second study, 310 patients were randomized.

Both protocols stipulated that first Day 1 dose would be given under supervision, with an initial dose of buprenorphine 2 mg or ZUBSOLV 1.4 mg. Subsequently, investigators were provided an option to give buprenorphine 6 mg or ZUBSOLV 4.2 mg as a single dose 1.5 hours after the second dose, or to divide the second dose of study medication into 3 separate dosing occasions of ZUBSOLV 1.4 mg/0.36 mg or generic buprenorphine 2 mg each, 1 to 2 hours between doses, if there was precipitated withdrawal after the first dose, as assessed by the investigator. The option to divide the second dose was used at the discretion of the investigators only rarely in Study 2 (5%), compared to more frequent use in Study 1 (22%).

Results for Day 3 retention rate from each study are presented in Table 6. The lower rate of retention on Day 3 observed for ZUBSOLV in comparison to generic buprenorphine in Study 2 may be attributable to the infrequent use of divided dosing.

Table 6. Retention at Day 3 (full analysis set)
Study 1
Number in population | ZUBSOLV (N=383) | Generic BUP (N=375) | Overall (N=758)
Retention at Day 3 | 357 (93%) | 344 (92%) | 701 (93%)
Study 2
Number in population | ZUBSOLV (N=155) | Generic BUP (N=155) | Overall (N=310)
Retention at Day 3 | 132 (85%) | 147 (95%) | - (90%)

16 HOW SUPPLIED / STORAGE AND HANDLING

ZUBSOLV sublingual tablets are menthol-flavored white tablets supplied in aluminum/aluminum child resistant unit dose blister packages. ZUBSOLV is available in six dosage strengths imprinted in their respective buprenorphine strength

- Buprenorphine 0.7 mg /naloxone 0.18 mg, oval shape, imprinted with “.7”
- Buprenorphine 1.4 mg /naloxone 0.36 mg, triangular shape, imprinted with “1.4”
- Buprenorphine 2.9 mg /naloxone 0.71mg, D shape, imprinted with “2.9”
- Buprenorphine 5.7 mg /naloxone 1.4 mg, round shape, imprinted with “5.7”
- Buprenorphine 8.6 mg /naloxone 2.1 mg, diamond shape, imprinted with “8.6”
- Buprenorphine 11.4 mg /naloxone 2.9 mg, capsule shape, imprinted with “11.4”

- NDC 54123-907-30 (buprenorphine 0.7 mg /naloxone 0.18 mg) sublingual tablet – 3x10 tablets per carton
- NDC 54123-914-30 (buprenorphine 1.4 mg /naloxone 0.36 mg) sublingual tablet – 3x10 tablets per carton
- NDC 54123-929-30 (buprenorphine 2.9 mg /naloxone 0.71 mg) sublingual tablet – 3x10 tablets per carton
- NDC 54123-957-30 (buprenorphine 5.7 mg /naloxone 1.4 mg) sublingual tablet – 3x10 tablets per carton
- NDC 54123-986-30 (buprenorphine 8.6 mg /naloxone 2.1 mg) sublingual tablet – 3x10 tablets per carton
- NDC 54123-114-30 (buprenorphine 11.4 mg /naloxone 2.9 mg) sublingual tablet – 3x10 tablets per carton

Store at 20-25°C (68-77°F), excursions permitted to 15-30°C (59-86°F) [see USP Controlled Room Temperature]

Store ZUBSOLV securely and dispose of properly [see Patient Counseling Information (17)].

17 PATIENT COUNSELING INFORMATION

Storage and Disposal

Because of the risks associated with accidental ingestion, misuse, and abuse, advise patients to store ZUBSOLV securely, out of sight and reach of children, and in a location not accessible by others, including visitors to the home [see Warnings and Precautions (5.1, 5.2, 5.4, 5.11), Drug Abuse and Dependence (9.2)]. Inform patients that leaving ZUBSOLV unsecured can pose a deadly risk to others in the home.

Advise patients and caregivers that when medicines are no longer needed, they should be disposed of promptly. Expired, unwanted, or unused ZUBSOLV should be disposed of by flushing the unused medication down the toilet if a drug take-back option is not readily available. Inform patients that they can visit www.fda.gov/drugdisposal for a complete list of medicines recommended for disposal by flushing, as well as additional information on disposal of unused medicines.

Advise patients to read the FDA-approved patient labeling. (Medication Guide)

Safe Use

Before initiating treatment with ZUBSOLV, explain the points listed below to caregivers and patients. Instruct patients to read the Medication Guide each time ZUBSOLV is dispensed because new information may be available.

- ZUBSOLV must be administered whole. Advise patients not to cut, chew, or swallow ZUBSOLV.
- Inform patients and caregivers that potentially fatal additive effects may occur if ZUBSOLV is used with benzodiazepines or other CNS depressants (e.g., alcohol, non-benzodiazepines, sedative/hypnotics, anxiolytics, tranquilizers, muscle relaxants, general anesthetics, antipsychotics, gabapentinoids [gabapentin or pregabalin], and other opioids) and not to use these concomitantly unless supervised by a healthcare provider [see Warnings and Precautions (5.2, 5.3), Drug Interactions (7)].
- Educate patients and caregivers on how to recognize respiratory depression and emphasize the importance of calling 911 or getting emergency medical help right away in the event of a known or suspected overdose [see Warnings and Precautions (5.2)].
- Patient Access to an Opioid Overdose Reversal Agent for the Emergency Treatment of Opioid Overdose

Inform patients and caregivers about opioid overdose reversal agents (e.g., naloxone, nalmefene) and discuss the importance of having access to an opioid overdose reversal agent. Because patients being treated for opioid use disorder are at risk for relapse, discuss the importance of having access to an opioid overdose reversal agent. Also discuss the importance of having access to an opioid overdose reversal agent if there are household members (including children) or other close contacts at risk for accidental ingestion or opioid overdose.

Discuss with the patient the options for obtaining an opioid overdose reversal agent (e.g., prescription, over-the-counter (some products), or as part of a community-based program) [see Dosage and Administration (2.2), Warnings and Precautions (5.2)].

There are important differences among the opioid overdose reversal agents. Be familiar with these differences, as outlined in the approved labeling for those products, prior to recommending or prescribing such an agent.

Educate patients and caregivers on how to recognize the signs and symptoms of an opioid overdose.

Explain to patients and caregivers that effects of opioid overdose reversal agents like naloxone and nalmefene are temporary, and that they must call 911 or get emergency medical help right away in all cases of known or suspected opioid overdose, even if an opioid overdose reversal agent is administered. Repeat administration may be necessary, particularly for overdose involving buprenorphine [Dosage and Administration (2.2), Warnings and Precautions (5.2), Overdosage (10)].

Advise patients and caregivers:

• how to treat with an opioid overdose reversal agent in the event of an opioid overdose

• to tell family and friends about their opioid overdose reversal agent, and to keep it in a place where family and friends can easily access it in an emergency

• to read the Patient Information (or other educational material) that will come with their opioid overdose reversal agent. Emphasize the importance of doing this before an opioid emergency happens, so the patient and caregiver will know what to do.

- Advise patients that ZUBSOLV contain an opioid that can be a target for people who abuse prescription medications or street drugs, to keep their tablets in a safe place, and to protect them from theft.
- Instruct patients to keep ZUBSOLV in a secure place, out of the sight and reach of children. Accidental or deliberate ingestion by a child may cause respiratory depression that can result in death. Advise patients to seek medical attention immediately if a child is exposed to ZUBSOLV.
- Inform patients that opioids could cause a rare but potentially life-threatening condition resulting from concomitant administration of serotonergic drugs. Warn patients of the symptoms of serotonin syndrome and to seek medical attention right away if symptoms develop. Instruct patients to inform their healthcare providers if they are taking, or plan to take serotonergic medications [see Drug Interactions (7)].
- Inform patients that opioids could cause adrenal insufficiency, a potentially life-threatening condition. Adrenal insufficiency may present with non-specific symptoms and signs such as nausea, vomiting, anorexia, fatigue, weakness, dizziness, and low blood pressure. Advise patients to seek medical attention if they experience a constellation of these symptoms [see Warnings and Precautions (5.6)].
- Advise patients to never give ZUBSOLV to anyone else, even if he or she has the same signs and symptoms. It may cause harm or death.
- Advise patients that selling or giving away this medication is against the law.
- Advise patients that, after ZUBSOLV has completely dissolved in the oral mucosa, to take a sip of water, swish it gently around their teeth and gums, and swallow. Advise patients to wait for at least one hour after taking ZUBSOLV before brushing teeth [see Warnings and Precautions (5.13)].
- Refer patients to dental care services and encourage them to have regular dental checkups while taking ZUBSOLV. Instruct patients to inform their dentist that they have started therapy on ZUBSOLV [see Warnings and Precautions (5.13)].
- Caution patients that ZUBSOLV may impair the mental or physical abilities required for the performance of potentially dangerous tasks such as driving or operating machinery. Caution should be taken especially during drug induction and dose adjustment and until individuals are reasonably certain that buprenorphine therapy does not adversely affect their ability to engage in such activities [see Warnings and Precautions (5.15)].
- Advise patients not to change the dosage of ZUBSOLV without consulting their healthcare provider.
- Advise patients to take ZUBSOLV once a day, after induction.
- Advise patients that if they miss a dose of ZUBSOLV they should take it as soon as they remember. If it is almost time for the next dose, they should skip the missed dose and take the next dose at the regular time.
- Inform patients that ZUBSOLV can cause drug dependence and that withdrawal signs and symptoms may occur when the medication is discontinued.
- Advise patients seeking to discontinue treatment with buprenorphine for opioid dependence should be advised to work closely with their healthcare provider on a tapering schedule and inform them of the potential to relapse to illicit drug use associated with discontinuation of opioid agonist/partial agonist medication-assisted treatment.
- Advise patients that, like other opioids, ZUBSOLV may produce orthostatic hypotension in ambulatory individuals [see Warnings and Precautions. (5.16)].
- Advise patients to inform their healthcare provider if any other prescription medications, over-the-counter medications, or herbal preparations are prescribed or currently being used [see Drug Interactions (7)].
- Advise women that if they are pregnant while being treated with ZUBSOLV, the baby may have signs of withdrawal at birth and that withdrawal is treatable [see Warnings and Precautions (5.5), Use in Specific Populations (8.1)].
- Advise women who are breastfeeding to monitor the infant for drowsiness and difficulty breathing [see Use in Specific Populations (8.2)].
- Inform patients that chronic use of opioids may cause reduced fertility. It is not known whether these effects on fertility are reversible [see Adverse Reactions (6.2)].
- Advise patients to inform their family members that, in the event of emergency, the treating healthcare provider or emergency room staff should be informed that the patient is physically dependent on an opioid and that the patient is being treated with ZUBSOLV.

Manufactured for and distributed by Orexo US, Inc.
Morristown, NJ 07960 USA

For patent information: https://orexo.com/treatments/treatment-portfolio/#zubsolv

ZUBSOLV is a licensed trademark of Orexo US, Inc.
© 2025 Orexo US, Inc. All rights reserved.
Suboxone® is a registered trademark of Indivior UK Limited

Medication Guide
ZUBSOLV®
(Zub-solve) (buprenorphine and naloxone) Sublingual Tablet, CIII

IMPORTANT: Keep ZUBSOLV in a secure place away from children. Accidental use by a child is a medical emergency and can result in death. If a child accidentally uses ZUBSOLV, get emergency help or call 911 right away. Tell your healthcare provider if you are living in a household where there are small children.

What is the most important information I should know about ZUBSOLV?

- ZUBSOLV contains a medicine called buprenorphine. Buprenorphine is an opioid that can cause serious and life-threatening breathing problems, especially if you take or use certain other medicines or drugs.
- Ask your healthcare provider about medications like naloxone or nalmefene that can be used in an emergency to reverse opioid overdose including accidental use of ZUBSOLV sublingual tablet by a child. If naloxone or nalmefene is given, you must call 911 or get emergency medical help right away to treat an overdose or accidental use of an opioid.
- ZUBSOLV may cause serious and life-threatening breathing problems. Get emergency help right away if:
  ◦ feel faint
  ◦ feel dizzy
  ◦ are confused
  ◦ feel sleepy or uncoordinated
  ◦ have blurred vision
  ◦ have slurred speech
  ◦ are breathing slower than normal
  ◦ cannot think well or clearly
- Do not take ZUBSOLV with certain medicines. Taking ZUBSOLV with other opioid medicines, benzodiazepines, gabapentinoids (gabapentin or pregabalin), alcohol, or other central nervous system depressants (including street drugs) can cause severe drowsiness, decreased awareness, breathing problems, coma, and death.
- Do not inject (“shoot-up”) ZUBSOLV. Injecting ZUBSOLV may cause life-threatening infections and other serious health problems, Injecting ZUBSOLV may cause sudden serious withdrawal symptoms such as pain, cramps, vomiting, diarrhea, anxiety, sleep problems, and cravings.
- Do not switch from ZUBSOLV to other medicines that contain buprenorphine without talking with your doctor. The amount of buprenorphine in a dose of ZUBSOLV is not the same as in other medicines that contain buprenorphine. Your healthcare provider will prescribe a starting dose of buprenorphine that may be different than other buprenorphine containing medicines you may have been taking.
- Do not stop taking ZUBSOLV suddenly. You could become sick and have withdrawal symptoms because your body has become used to the medicine (physical dependence). Physical dependence is not the same as drug addiction.
- In an emergency, have family members tell the emergency department staff that you are physically dependent on an opioid and are being treated with ZUBSOLV.
- Never give anyone else your ZUBSOLV. They could die from taking it. Selling or giving away ZUBSOLV is against the law.
- Store ZUBSOLV securely, out of sight and reach of children, and in a location not accessible by others, including visitors to the home.

What is ZUBSOLV?

- ZUBSOLV is a prescription medicine used to treat opioid addiction in adults and is part of a complete treatment program that also includes counseling and behavioral therapy.

Who should not take ZUBSOLV?
Do not take ZUBSOLV if you are allergic to buprenorphine or naloxone.

What should I tell my doctor before taking ZUBSOLV?
Before taking ZUBSOLV, tell your healthcare provider about all of your medical conditions, including if you have:

- trouble breathing or lung problems
- a curve in your spine that affects your breathing
- Addison’s disease
- an enlarged prostate (men)
- problems urinating
- liver, kidney, or gallbladder problems
- alcoholism
- a head injury or brain problem
- mental health problems
- adrenal gland or thyroid gland problems
- tooth problems, including a history of cavities

Tell your healthcare provider if you are:

- pregnant or plan to become pregnant. If you take ZUBSOLV while pregnant, your baby may have symptoms of opioid withdrawal at birth that could be life-threatening if not recognized and treated. Talk to your healthcare provider if you are pregnant or plan to become pregnant.
- breastfeeding. ZUBSOLV can pass into your breast milk and harm your baby. Talk to your healthcare provider about the best way to feed your baby if you take ZUBSOLV. Monitor your baby for increased drowsiness and breathing problems if you breastfeed during treatment with ZUBSOLV.

Tell your healthcare provider about all of the medicines you take, including prescription and over-the-counter medicines, vitamins, or herbal supplements.

How should I take ZUBSOLV?
Read the Instructions for Use at the end of this Medication Guide for detailed instructions on how to take ZUBSOLV

- Take ZUBSOLV exactly as prescribed by your healthcare provider. Your healthcare provider may change your dose after seeing how it affects you. Do not change your dose unless your healthcare provider tells you to change it.
- Do not take ZUBSOLV more often than prescribed by your healthcare provider.
- ZUBSOLV is not for occasional or “as needed” use
- You may be prescribed a dose of 2 or more ZUBSOLV sublingual tablets at the same time.
- After induction (your first day of dosing), take ZUBSOLV 1 time a day.
- Use the entire ZUBSOLV tablet. Do not cut, chew, or swallow the tablet.
- If you miss a dose of ZUBSOLV, take it as soon as you remember. If it is almost time for your next dose, skip the missed dose and take the next dose at your regular time. Do not take 2 doses at the same time unless your healthcare provider tells you to. If you are not sure about your dosing, call your healthcare provider.
- Dispose of expired, unwanted, or unused ZUBSOLV by promptly flushing down the toilet (if a drug take-back option is not readily available). Visit www.fda.gov/drugdisposal for additional information on disposal of unused medicines.
- If you take too much ZUBSOLV or overdose, get emergency medical help right away.
- After ZUBSOLV is completely dissolved, rinse your mouth with water and swallow. Wait for at least one hour before brushing teeth.
- Report any problems with your teeth immediately to your healthcare provider and schedule an appointment with a dentist. Tell your dentist that you have started taking ZUBSOLV.

What should I avoid while taking ZUBSOLV?

- Do not drive, operate heavy machinery, or perform any other dangerous activities until you know how ZUBSOLV affects you. Buprenorphine can cause drowsiness and slow reaction times. ZUBSOLV can make you sleepy, dizzy, or lightheaded.
- You should not drink alcohol or use prescription or over-the-counter medicines that contain alcohol while taking ZUBSOLV, because this can lead to loss of consciousness or even death.

What are the possible side effects of ZUBSOLV?
ZUBSOLV can cause serious side effects, including:

- Trouble breathing. Taking ZUBSOLV with other opioid medicines, benzodiazepines, gabapentinoids (gabapentin or pregabalin), alcohol, or other central nervous system depressants can cause breathing problems that can lead to coma and death.
- Sleepiness, dizziness, and problems with coordination.
- Physical dependence or abuse.
- Liver problems. Call your healthcare provider right away if you notice any of these symptoms:
- your skin or the white part of your eyes turns yellow (jaundice)
- dark or “tea-colored” urine
- light colored stools (bowel movements)
- loss of appetite
- pain, aching, or tenderness on the right side of your stomach area
- nausea
- Your healthcare provider should do blood tests to check the liver before you start taking and while you take ZUBSOLV.
- Your healthcare provider should do blood tests to check the liver before you start taking and while you take ZUBSOLV.
- Allergic reaction. You may have a rash, hives, swelling of your face, wheezing, low blood pressure, or loss of consciousness. Call your healthcare provider or get emergency help right away.
- Opioid withdrawal. Call your healthcare provider right away if you get any of these symptoms:
- Shaking
- Sweating more than normal
- Feeling hot or cold more than normal
- runny nose
- watery eyes
- goose bumps
- diarrhea
- vomiting
- muscle aches
- Decrease in blood pressure. You may feel dizzy if you get up too fast from sitting or lying down.
- The most common side effects of ZUBSOLV include:
- Headache
- nausea
- vomiting
- constipation
- pain
- increased sweating
- decrease in sleep (insomina)
- ZUBSOLV sublingual tablet may affect fertility in males and females. Talk to your healthcare provider if this is a concern for you.
- These are not all the possible side effects of ZUBSOLV.

Call your doctor for medical advice about side effects. You may report side effects to FDA at 1-800-FDA-1088.

General information about the safe and effective use of ZUBSOLV.
Medicines are sometimes prescribed for purposes other than those listed in a Medication Guide. Do not use ZUBSOLV for a condition for which it was not prescribed. Do not give ZUBSOLV to other people, even if they have the same symptoms you have. It may harm them and it is against the law. You can ask your doctor or pharmacist for information that is written for health professionals.

Manufactured for and distributed by Orexo US, Inc. Morristown, NJ 07960 USA
ZUBSOLV is a licensed trademark of Orexo US, Inc.© 2025 Orexo US, Inc. All rights reserved.
Printed in USA

This Medication Guide has been approved by the U.S. Food and Drug Administration. Revised: 12/2025

PATIENT INFORMATION

INSTRUCTIONS FOR USE

ZUBSOLV® (Zub-solve) (buprenorphine and naloxone) Sublingual Tablet, CIII

This “Instructions for Use” contains information on how to correctly take ZUBSOLV sublingual tablets.

Important Information You Need to Know Before Taking ZUBSOLV sublingual tablets:

- Your healthcare provider should show you how to take ZUBSOLV sublingual tablets the right way.

Preparing to take ZUBSOLV sublingual tablets:

- Follow the same instructions every time you take a dose of ZUBSOLV.
- ZUBSOLV comes in a blister pack with 10 blister units. Each blister unit contains a ZUBSOLV tablet.
- Take the dose prescribed by your doctor as follows:
  ◦ Pull apart 1 of the blister units from the blister pack by tearing along the dotted lines (perforations) until it is fully separated (See Figure A).

◦ When the blister unit is fully separated, fold the single unit down at dotted line toward the blister (See Figure B).

◦ Slowly tear down at notch to open the blister unit (See Figure C).

◦ Do not push ZUBSOLV tablets through the foil. This could cause the tablet to break.

◦ As soon as you remove your prescribed dose of ZUBSOLV from the blister pack place the tablet under your tongue (See Figures D, E, and F). If more than 1 tablet is required, place the tablets in different places under your tongue at the same time.

◦ Let the tablet dissolve completely. ZUBSOLV usually dissolves in your mouth within 5 minutes. If your mouth is dry, take a sip of water to moisten it. Spit out or swallow the water and dry your hands if they are wet before you place the ZUBSOLV tablet under your tongue.

- While ZUBSOLV is dissolving, do not chew or swallow the tablet because the medicine will not work as well.
- Do not eat or drink anything until the ZUBSOLV tablet has completely dissolved.
- Talking while the tablet is dissolving can affect how well the medicine in ZUBSOLV is absorbed.
- After ZUBSOLV is completely dissolved, rinse your mouth with water and swallow. Wait for at least one hour before brushing teeth.
- If you miss a dose of ZUBSOLV, take your medicine when you remember. If it is almost time for your next dose, skip the missed dose and take the next dose at your regular time. Do not take 2 doses at the same time unless your doctor tells you to. If you are not sure about your dosing, call your doctor.
- Do not stop taking ZUBSOLV suddenly. You could become sick and have withdrawal symptoms because your body has become used to the medicine. Physical dependence is not the same as drug addiction. Your doctor can tell you more about the differences between physical dependence and drug addiction. To have fewer withdrawal symptoms, ask your doctor how to stop using ZUBSOLV the right way.

If you take too much ZUBSOLV go to the nearest hospital emergency room right away.

Storing ZUBSOLV sublingual tablets?

- Store ZUBSOLV at room temperature between 68°F to 77°F (20°C to 25°C).
- Keep ZUBSOLV in a safe place, out of the sight and reach of children.

Disposing of ZUBSOLV sublingual tablets?

- Dispose of expired, unwanted, or unused ZUBSOLV by promptly flushing down the toilet, if a drug take-back option is not readily available. Visit www.fda.gov/drugdisposal for additional information on disposal of unused medicines.

This Instructions for Use has been approved by the U.S. Food and Drug Administration.

Revised: 06/2022

PRINCIPAL DISPLAY PANEL

NDC 54123-907-30
Rx Only
CIII
zubsolv®
(buprenorphine and naloxone) sublingual tablets
0.7 mg/0.18 mg
Menthol Flavor
For Sublingual Administration.
Do Not Cut, Crush, Break, Chew, or Swallow Tablet.
Keep ZUBSOLV in a safe place, out of the sight and reach of children. Buprenorphine can cause severe, possibly fatal, respiratory depression in children. Children who accidentally take ZUBSOLV will require immediate medical attention.
Read enclosed ZUBSOLV Medication Guide for Important Safety Information.
30 Sublingual Tablets
(10 tablets x3 cards)
www.zubsolv.com

PRINCIPAL DISPLAY PANEL

NDC 54123-914-30
Rx Only
CIII
zubsolv®
(buprenorphine and naloxone) sublingual tablets
1.4 mg/0.36 mg
Menthol Flavor
For Sublingual Administration.
Do Not Cut, Crush, Break, Chew, or Swallow Tablet.
Keep ZUBSOLV in a safe place, out of the sight and reach of children. Buprenorphine can cause severe, possibly fatal, respiratory depression in children. Children who accidentally take ZUBSOLV will require immediate medical attention.
Read enclosed ZUBSOLV Medication Guide for Important Safety Information.
30 Sublingual Tablets
(10 tablets x3 cards)
www.zubsolv.com

PRINCIPAL DISPLAY PANEL

NDC 54123-929-30

Rx Only

CIII

zubsolv®

(buprenorphine and naloxone) sublingual tablets

2.9 mg/0.71 mg

Menthol Flavor

For Sublingual Administration.

Do Not Cut, Crush, Break, Chew, or Swallow Tablet.

Keep ZUBSOLV in a safe place, out of the sight and reach

of children. Buprenorphine can cause severe, possibly fatal,

respiratory depression in children. Children who accidentally

take ZUBSOLV will require immediate medical attention.

Read enclosed ZUBSOLV Medication Guide

for Important Safety Information.

30 Sublingual Tablets

(10 tablets x3 cards)

www.zubsolv.com

PRINCIPAL DISPLAY PANEL

NDC 54123-957-30
Rx Only
CIII
zubsolv®
(buprenorphine and naloxone) sublingual tablets
5.7 mg/1.4 mg
Menthol Flavor
For Sublingual Administration.
Do Not Cut, Crush, Break, Chew, or Swallow Tablet.
Keep ZUBSOLV in a safe place, out of the sight and reach of children. Buprenorphine can cause severe, possibly fatal, respiratory depression in children. Children who accidentally take ZUBSOLV will require immediate medical attention.
Read enclosed ZUBSOLV Medication Guide for Important Safety Information.
30 Sublingual Tablets
(10 tablets x3 cards)
www.zubsolv.com

PRINCIPAL DISPLAY PANEL

NDC 54123-986-30
Rx Only
CIII
zubsolv®
(buprenorphine and naloxone) sublingual tablets
8.6 mg/2.1 mg
Menthol Flavor
For Sublingual Administration.
Do Not Cut, Crush, Break, Chew, or Swallow Tablet.
Keep ZUBSOLV in a safe place, out of the sight and reach of children. Buprenorphine can cause severe, possibly fatal, respiratory depression in children. Children who accidentally take ZUBSOLV will require immediate medical attention.
Read enclosed ZUBSOLV Medication Guide for Important Safety Information.
30 Sublingual Tablets
(10 tablets x3 cards)
www.zubsolv.com

PRINCIPAL DISPLAY PANEL

NDC 54123-114-30
Rx Only
CIII
zubsolv®
(buprenorphine and naloxone) sublingual tablets
11.4 mg/2.9 mg
Menthol Flavor
For Sublingual Administration.
Do Not Cut, Crush, Break, Chew, or Swallow Tablet.
Keep ZUBSOLV in a safe place, out of the sight and reach of children. Buprenorphine can cause severe, possibly fatal, respiratory depression in children. Children who accidentally take ZUBSOLV will require immediate medical attention.
Read enclosed ZUBSOLV Medication Guide for Important Safety Information.
30 Sublingual Tablets
(10 tablets x3 cards)
www.zubsolv.com